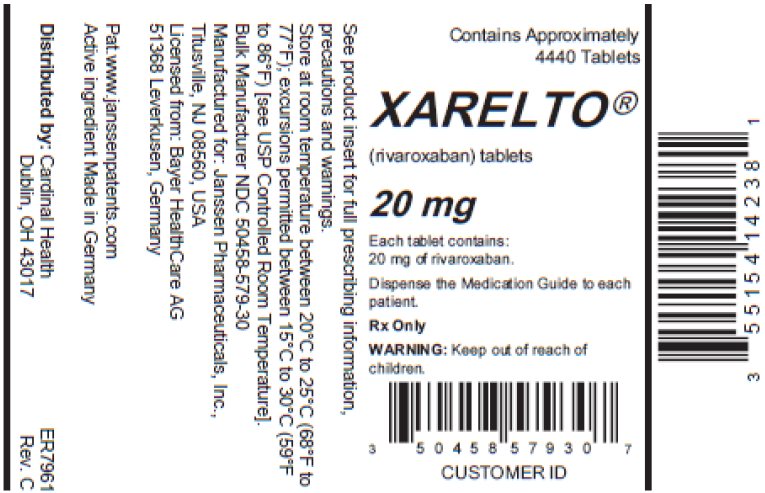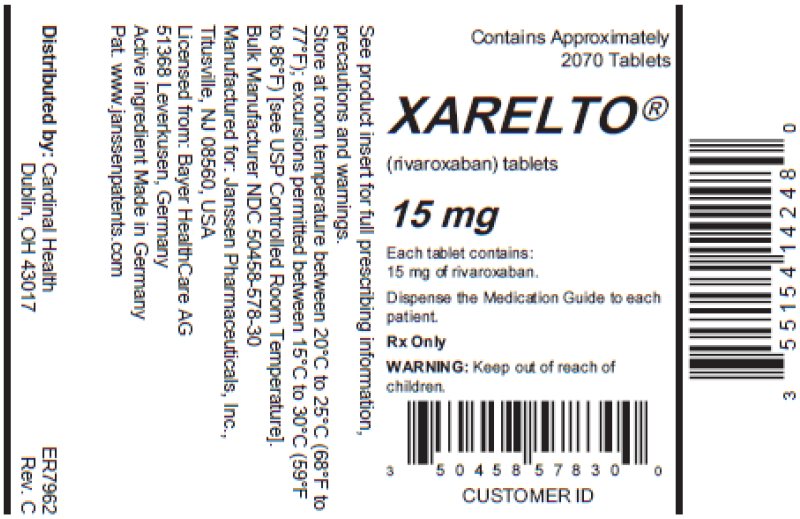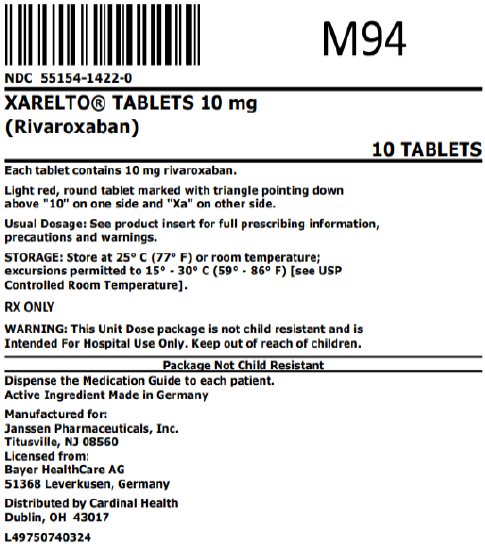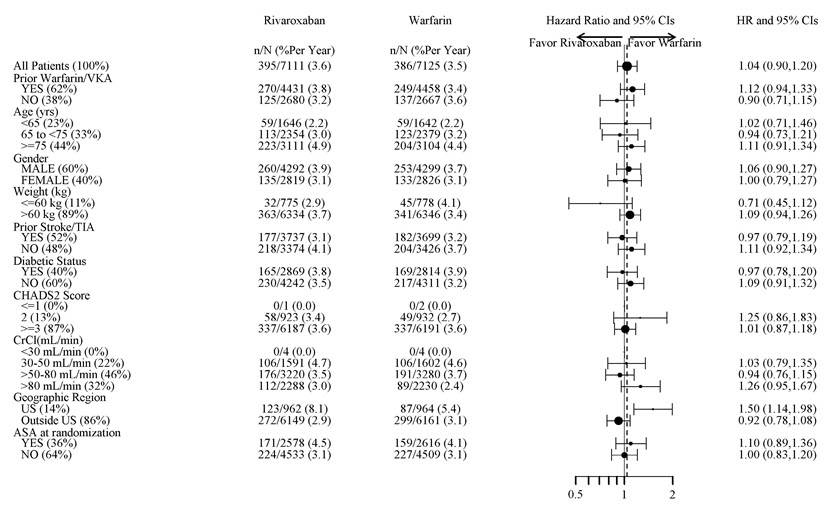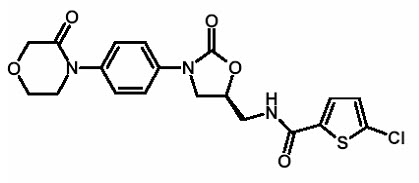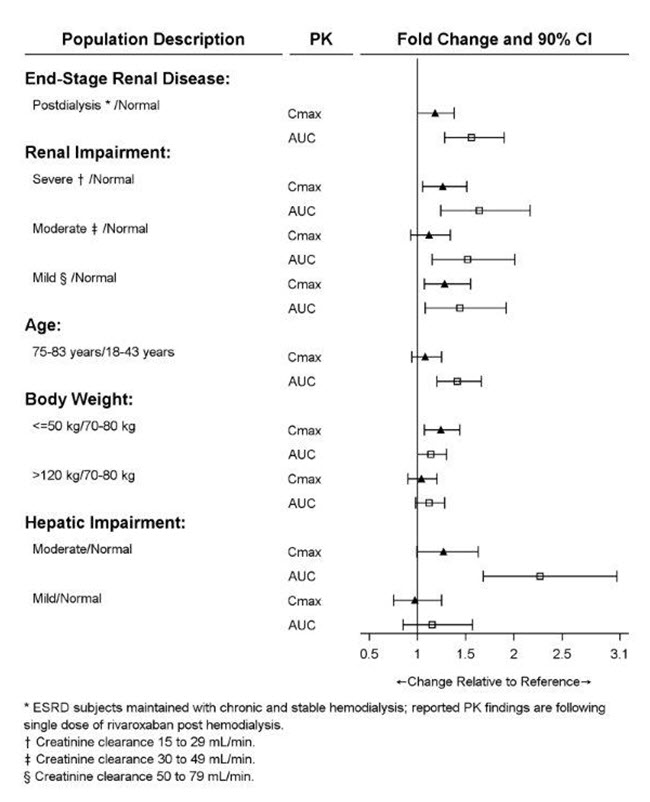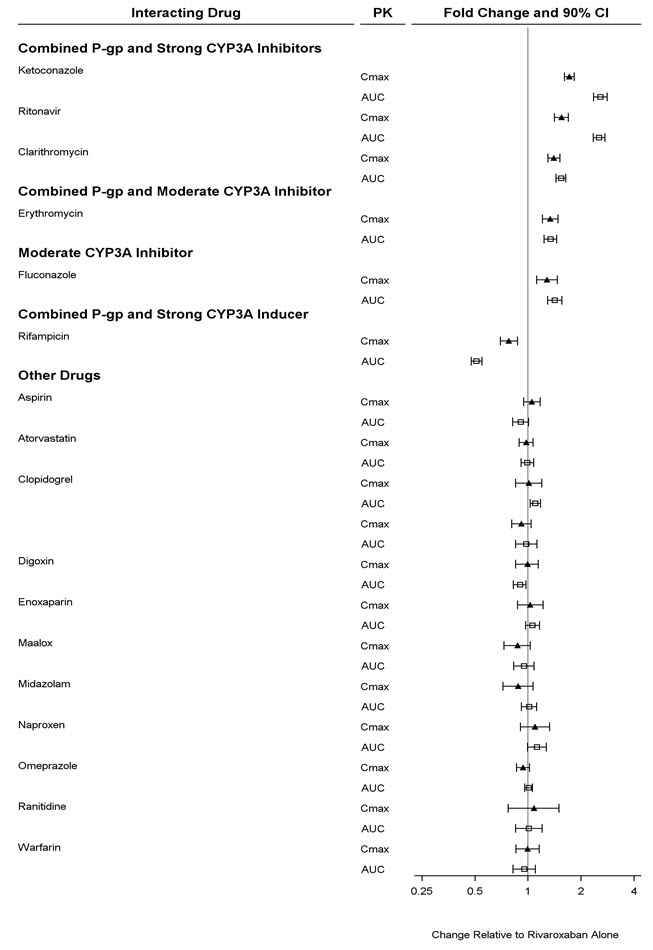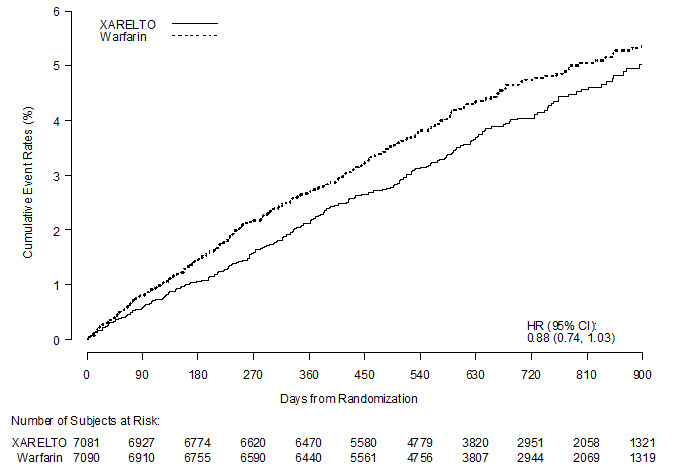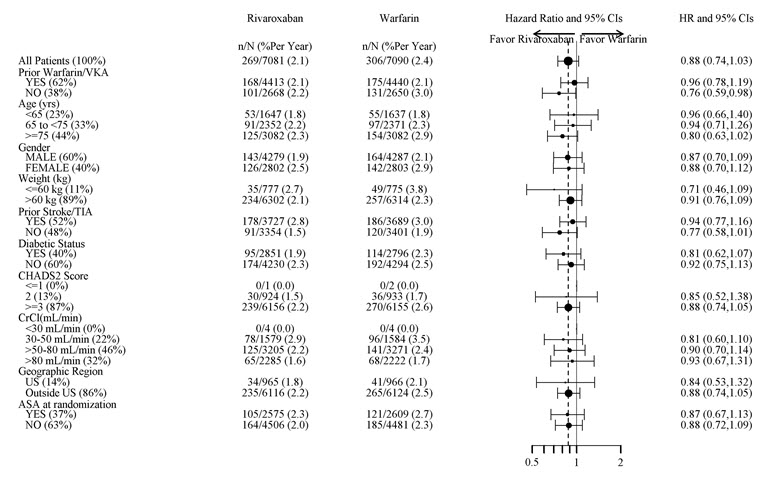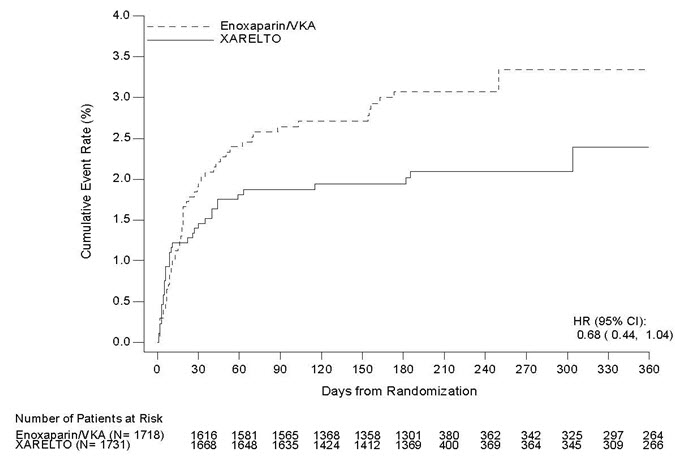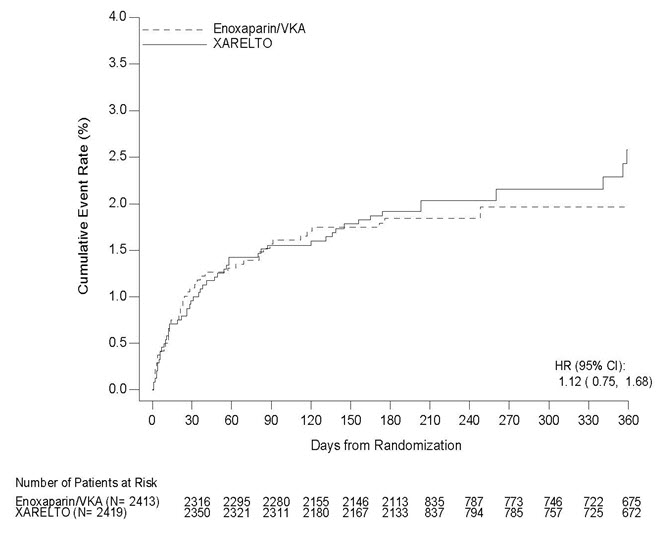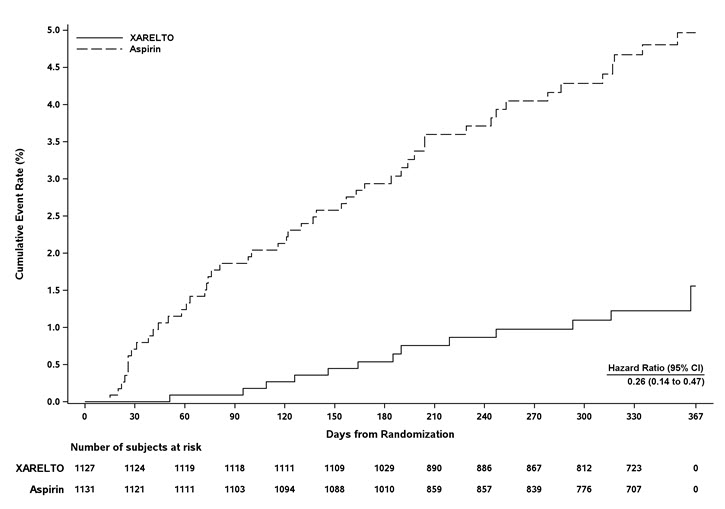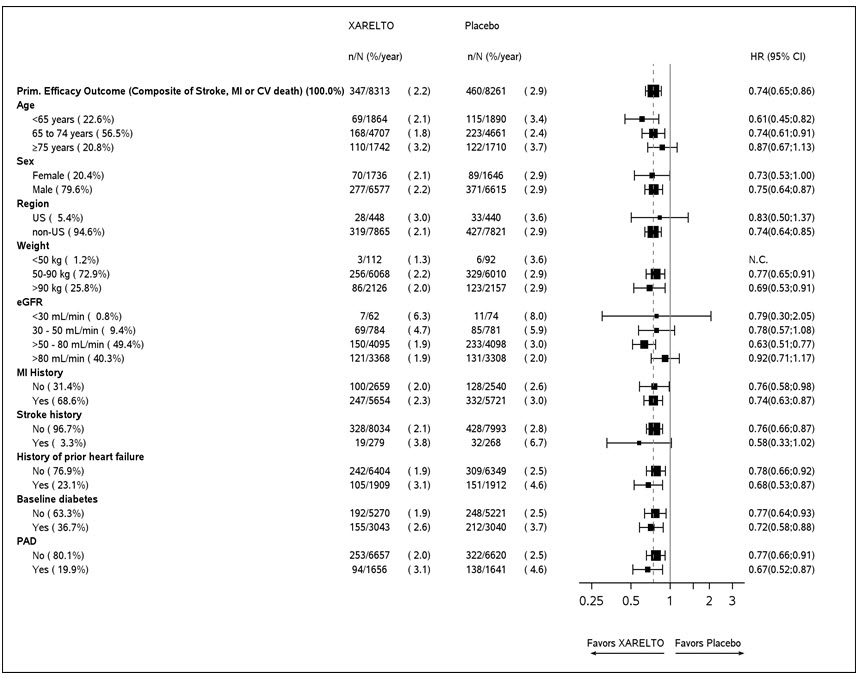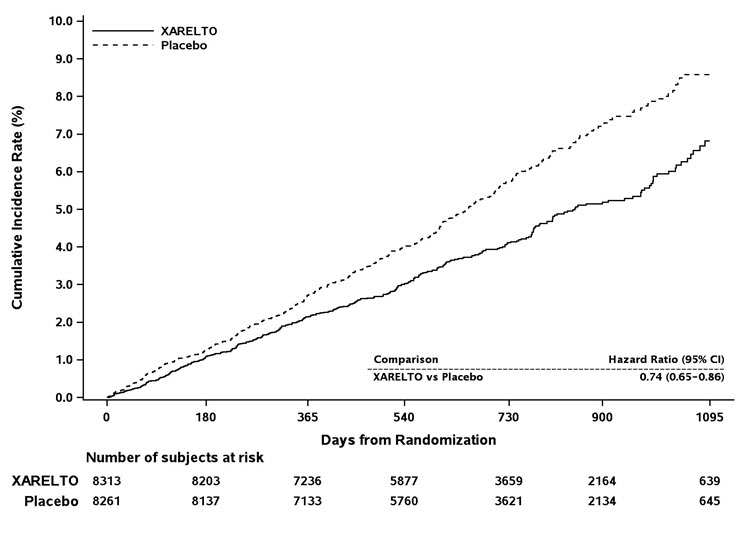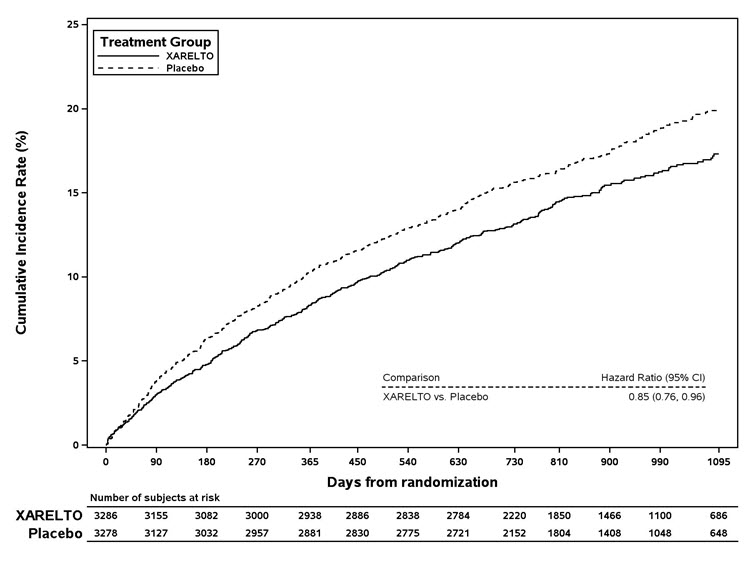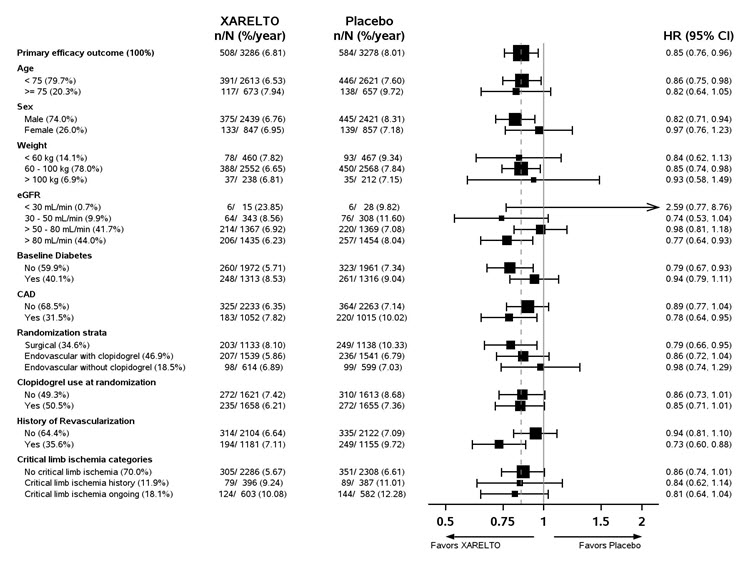 DRUG LABEL: Xarelto
NDC: 55154-1422 | Form: TABLET, FILM COATED
Manufacturer: Cardinal Health 107, LLC
Category: prescription | Type: HUMAN PRESCRIPTION DRUG LABEL
Date: 20260217

ACTIVE INGREDIENTS: RIVAROXABAN 10 mg/1 1
INACTIVE INGREDIENTS: CROSCARMELLOSE SODIUM; HYPROMELLOSE, UNSPECIFIED; LACTOSE MONOHYDRATE; MAGNESIUM STEARATE; MICROCRYSTALLINE CELLULOSE; SODIUM LAURYL SULFATE; FERRIC OXIDE RED; POLYETHYLENE GLYCOL 3350; TITANIUM DIOXIDE

HIGHLIGHTS OF PRESCRIBING INFORMATION

These highlights do not include all the information needed to use XARELTO safely and effectively. See full prescribing information for XARELTO.
XARELTO ®(rivaroxaban) tablets, for oral use
XARELTO ®(rivaroxaban) for oral suspension
Initial U.S. Approval: 2011

WARNING: (A) PREMATURE DISCONTINUATION OF XARELTO INCREASES THE RISK OF THROMBOTIC EVENTS, (B) SPINAL/EPIDURAL HEMATOMA

See full prescribing information for complete boxed warning.

(A) Premature discontinuation of XARELTO increases the risk of thrombotic events

Premature discontinuation of any oral anticoagulant, including XARELTO, increases the risk of thrombotic events. To reduce this risk, consider coverage with another anticoagulant if XARELTO is discontinued for a reason other than pathological bleeding or completion of a course of therapy. (2.2, 2.3, 5.1, 14.1)

(B) Spinal/epidural hematoma

Epidural or spinal hematomas have occurred in patients treated with XARELTO who are receiving neuraxial anesthesia or undergoing spinal puncture. These hematomas may result in long-term or permanent paralysis. (5.2, 5.3, 6.2)

Monitor patients frequently for signs and symptoms of neurological impairment and if observed, treat urgently. Consider the benefits and risks before neuraxial intervention in patients who are or who need to be anticoagulated. (5.3)

RECENT MAJOR CHANGES

Warnings and Precautions (5.2) | 06/2025

1 INDICATIONS AND USAGE

XARELTO is a factor Xa inhibitor indicated:

- to reduce risk of stroke and systemic embolism in nonvalvular atrial fibrillation (1.1)
- for treatment of deep vein thrombosis (DVT) (1.2)
- for treatment of pulmonary embolism (PE) (1.3)
- for reduction in the risk of recurrence of DVT or PE (1.4)
- for the prophylaxis of DVT, which may lead to PE in patients undergoing knee or hip replacement surgery (1.5)
- for prophylaxis of venous thromboembolism (VTE) in acutely ill medical patients (1.6)
- to reduce the risk of major cardiovascular events in patients with coronary artery disease (CAD) (1.7)
- to reduce the risk of major thrombotic vascular events in patients with peripheral artery disease (PAD), including patients after recent lower extremity revascularization due to symptomatic PAD (1.8)
- for treatment of VTE and reduction in the risk of recurrent VTE in pediatric patients from birth to less than 18 years (1.9)
- for thromboprophylaxis in pediatric patients 2 years and older with congenital heart disease after the Fontan procedure (1.10)

2 DOSAGE AND ADMINISTRATION

- Nonvalvular Atrial Fibrillation: 15 or 20 mg, once daily with food (2.1)
- Treatment of DVT and/or PE: 15 mg orally twice daily with food for the first 21 days followed by 20 mg orally once daily with food for the remaining treatment (2.1)
- Reduction in the Risk of Recurrence of DVT and/or PE in patients at continued risk for DVT and/or PE: 10 mg once daily with or without food, after at least 6 months of standard anticoagulant treatment (2.1)
- Prophylaxis of DVT Following Hip or Knee Replacement Surgery: 10 mg orally once daily with or without food (2.1)
- Prophylaxis of VTE in Acutely Ill Medical Patients at Risk for Thromboembolic Complications Not at High Risk of Bleeding: 10 mg once daily, with or without food, in hospital and after hospital discharge for a total recommended duration of 31 to 39 days (2.1)
- CAD or PAD: 2.5 mg orally twice daily with or without food, in combination with aspirin (75–100 mg) once daily (2.1)
- Pediatric Patients:See dosing recommendations in the Full Prescribing Information (2.2)

3 DOSAGE FORMS AND STRENGTHS

- Tablets: 2.5 mg, 10 mg, 15 mg, and 20 mg (3)
- For oral suspension: 1 mg/mL once reconstituted (3)

4 CONTRAINDICATIONS

- Active pathological bleeding (4)
- Severe hypersensitivity reaction to XARELTO (4)

5 WARNINGS AND PRECAUTIONS

- Risk of bleeding: XARELTO can cause serious and fatal bleeding. An agent to reverse the activity of rivaroxaban is available. (5.2)
- Pregnancy-related hemorrhage: Use XARELTO with caution in pregnant women due to the potential for obstetric hemorrhage and/or emergent delivery. (5.7, 8.1)
- Prosthetic heart valves: XARELTO use not recommended. (5.8)
- Increased Risk of Thrombosis in Patients with Triple Positive Antiphospholipid Syndrome: XARELTO use not recommended. (5.10)

6 ADVERSE REACTIONS

- The most common adverse reaction (>5%) in adult patients was bleeding. (6.1)
- The most common adverse reactions (>10%) in pediatric patients were bleeding, cough, vomiting, and gastroenteritis. (6.1)

To report SUSPECTED ADVERSE REACTIONS, contact Janssen Pharmaceuticals, Inc. at 1-800-526-7736 or FDA at 1-800-FDA-1088 or www.fda.gov/medwatch.

7 DRUG INTERACTIONS

- Avoid combined P-gp and strong CYP3A inhibitors and inducers (7.2, 7.3)
- Anticoagulants: Avoid concomitant use (7.4)

8 USE IN SPECIFIC POPULATIONS

- Renal impairment: Avoid or adjust dose (8.6)
- Hepatic impairment: Avoid use in Child-Pugh B and C hepatic impairment or hepatic disease associated with coagulopathy (8.7)

FULL PRESCRIBING INFORMATION

WARNING: (A) PREMATURE DISCONTINUATION OF XARELTO INCREASES THE RISK OF THROMBOTIC EVENTS, (B) SPINAL/EPIDURAL HEMATOMA

A. Premature discontinuation of XARELTO increases the risk of thrombotic events

Premature discontinuation of any oral anticoagulant, including XARELTO, increases the risk of thrombotic events. If anticoagulation with XARELTO is discontinued for a reason other than pathological bleeding or completion of a course of therapy, consider coverage with another anticoagulant [see Dosage and Administration (2.3, 2.4), Warnings and Precautions (5.1), and Clinical Studies (14.1)].

B. Spinal/epidural hematoma

Epidural or spinal hematomas have occurred in patients treated with XARELTO who are receiving neuraxial anesthesia or undergoing spinal puncture. These hematomas may result in long-term or permanent paralysis. Consider these risks when scheduling patients for spinal procedures. Factors that can increase the risk of developing epidural or spinal hematomas in these patients include:

- use of indwelling epidural catheters
- concomitant use of other drugs that affect hemostasis, such as non-steroidal anti-inflammatory drugs (NSAIDs), platelet inhibitors, other anticoagulants
- a history of traumatic or repeated epidural or spinal punctures
- a history of spinal deformity or spinal surgery
- optimal timing between the administration of XARELTO and neuraxial procedures is not known

[see Warnings and Precautions (5.2, 5.3) and Adverse Reactions (6.2)].

Monitor patients frequently for signs and symptoms of neurological impairment. If neurological compromise is noted, urgent treatment is necessary [see Warnings and Precautions (5.3)].

Consider the benefits and risks before neuraxial intervention in patients anticoagulated or to be anticoagulated for thromboprophylaxis [see Warnings and Precautions (5.3)].

1 INDICATIONS AND USAGE

1.1 Reduction of Risk of Stroke and Systemic Embolism in Nonvalvular Atrial Fibrillation

XARELTO is indicated to reduce the risk of stroke and systemic embolism in adult patients with nonvalvular atrial fibrillation.

There are limited data on the relative effectiveness of XARELTO and warfarin in reducing the risk of stroke and systemic embolism when warfarin therapy is well-controlled [see Clinical Studies (14.1)].

1.2 Treatment of Deep Vein Thrombosis

XARELTO is indicated for the treatment of deep vein thrombosis (DVT).

1.3 Treatment of Pulmonary Embolism

XARELTO is indicated for the treatment of pulmonary embolism (PE).

1.4 Reduction in the Risk of Recurrence of Deep Vein Thrombosis and/or Pulmonary Embolism

XARELTO is indicated for the reduction in the risk of recurrence of DVT and/or PE in adult patients at continued risk for recurrent DVT and/or PE after completion of initial treatment lasting at least 6 months.

1.5 Prophylaxis of Deep Vein Thrombosis Following Hip or Knee Replacement Surgery

XARELTO is indicated for the prophylaxis of DVT, which may lead to PE in adult patients undergoing knee or hip replacement surgery.

1.6 Prophylaxis of Venous Thromboembolism in Acutely Ill Medical Patients at Risk for Thromboembolic Complications Not at High Risk of Bleeding

XARELTO is indicated for the prophylaxis of venous thromboembolism (VTE) and VTE related death during hospitalization and post hospital discharge in adult patients admitted for an acute medical illness who are at risk for thromboembolic complications due to moderate or severe restricted mobility and other risk factors for VTE and not at high risk of bleeding [see Warnings and Precautions (5.2) and Clinical Studies (14.5)].

1.7 Reduction of Risk of Major Cardiovascular Events in Patients with Coronary Artery Disease (CAD)

XARELTO, in combination with aspirin, is indicated to reduce the risk of major cardiovascular events (cardiovascular death, myocardial infarction, and stroke) in adult patients with coronary artery disease.

1.8 Reduction of Risk of Major Thrombotic Vascular Events in Patients with Peripheral Artery Disease (PAD), Including Patients after Lower Extremity Revascularization due to Symptomatic PAD

XARELTO, in combination with aspirin, is indicated to reduce the risk of major thrombotic vascular events (myocardial infarction, ischemic stroke, acute limb ischemia, and major amputation of a vascular etiology) in adult patients with PAD, including patients who have recently undergone a lower extremity revascularization procedure due to symptomatic PAD.

1.9 Treatment of Venous Thromboembolism and Reduction in Risk of Recurrent Venous Thromboembolism in Pediatric Patients

XARELTO is indicated for the treatment of venous thromboembolism (VTE) and the reduction in the risk of recurrent VTE in pediatric patients from birth to less than 18 years after at least 5 days of initial parenteral anticoagulant treatment.

1.10 Thromboprophylaxis in Pediatric Patients with Congenital Heart Disease after the Fontan Procedure

XARELTO is indicated for thromboprophylaxis in pediatric patients aged 2 years and older with congenital heart disease who have undergone the Fontan procedure.

2 DOSAGE AND ADMINISTRATION

2.1 Recommended Dosage in Adults

Table 1: Recommended Dosage in Adults
Indication | Renal Considerations [Calculate CrCl based on actual weight. [See Warnings and Precautions (5.4) and Use in Specific Populations (8.6)]] | Dosage | Food/Timing [See Clinical Pharmacology (12.3)]
Reduction in Risk of Stroke in Nonvalvular Atrial Fibrillation | CrCl >50 mL/min | 20 mg once daily | Take with evening meal
Reduction in Risk of Stroke in Nonvalvular Atrial Fibrillation | CrCl ≤50 mL/min [Patients with CrCl <30 mL/min were not studied, but administration of XARELTO is expected to result in serum concentrations of rivaroxaban similar to those in patients with moderate renal impairment (CrCl 30 to <50 mL/min) [see Use in Specific Populations (8.6)]] | 15 mg once daily | Take with evening meal
Treatment of DVT and/or PE | CrCl ≥15 mL/min | 15 mg twice daily ▼ after 21 days, transition to ▼ 20 mg once daily | Take with food, at the same time each day
Treatment of DVT and/or PE | CrCl <15 mL/min | Avoid Use
Reduction in the Risk of Recurrence of DVT and/or PE in patients at continued risk for DVT and/or PE | CrCl ≥15 mL/min | 10 mg once daily, after at least 6 months of standard anticoagulant treatment | Take with or without food
Reduction in the Risk of Recurrence of DVT and/or PE in patients at continued risk for DVT and/or PE | CrCl <15 mL/min | Avoid Use
Prophylaxis of DVT Following:
- Hip Replacement Surgery [See Dosage and Administration (2.4)] | CrCl ≥15 mL/min | 10 mg once daily for 35 days, 6–10 hours after surgery once hemostasis has been established | Take with or without food
- Hip Replacement Surgery [See Dosage and Administration (2.4)] | CrCl <15 mL/min | Avoid Use
- Knee Replacement Surgery | CrCl ≥15 mL/min | 10 mg once daily for 12 days, 6–10 hours after surgery once hemostasis has been established | Take with or without food
- Knee Replacement Surgery | CrCl <15 mL/min | Avoid Use
Prophylaxis of VTE in Acutely Ill Medical Patients at Risk for Thromboembolic Complications Not at High Risk of Bleeding | CrCl ≥15 mL/min | 10 mg once daily, in hospital and after hospital discharge, for a total recommended duration of 31 to 39 days | Take with or without food
Prophylaxis of VTE in Acutely Ill Medical Patients at Risk for Thromboembolic Complications Not at High Risk of Bleeding | CrCl <15 mL/min | Avoid Use
Reduction of Risk of Major Cardiovascular Events (CV Death, MI, and Stroke) in CAD | No dose adjustment needed based on CrCl | 2.5 mg twice daily, plus aspirin (75–100 mg) once daily | Take with or without food
Reduction of Risk of Major Thrombotic Vascular Events in PAD, Including Patients after Lower Extremity Revascularization due to Symptomatic PAD | No dose adjustment needed based on CrCl | 2.5 mg twice daily, plus aspirin (75–100 mg) once daily. When starting therapy after a successful lower extremity revascularization procedure, initiate once hemostasis has been established. | Take with or without food

2.2 Recommended Dosage in Pediatric Patients

Treatment of Venous Thromboembolism and Reduction in Risk of Recurrent Venous Thromboembolism in Pediatric Patients

Table 2: Recommended Dosage in Pediatric Patients Birth to Less than 18 Years for Treatment of and Reduction in Risk of Recurrent VTE [Initiate XARELTO treatment following at least 5 days of initial parenteral anticoagulation therapy.] , [Patients <6 months of age should meet the following criteria: at birth were at least 37 weeks of gestation, have had at least 10 days of oral feeding, and weigh ≥2.6 kg at the time of dosing.]
Dosage Form | Body Weight | 1 mg XARELTO = 1 mL Suspension
Dosage Form | Body Weight | Dosage |  |  | Total Daily Dose [All doses should be taken with feeding or with food since exposures match that of 20 mg daily dose in adults.]
Dosage Form | Body Weight | Once a Day [Once a day: approximately 24 hours apart; 2 times a day: approximately 12 hours apart; 3 times a day: approximately 8 hours apart] | 2 Times a Day | 3 Times a Day
Oral Suspension Only | 2.6 kg to 2.9 kg |  |  | 0.8 mg | 2.4 mg
Oral Suspension Only | 3 kg to 3.9 kg |  |  | 0.9 mg | 2.7 mg
Oral Suspension Only | 4 kg to 4.9 kg |  |  | 1.4 mg | 4.2 mg
Oral Suspension Only | 5 kg to 6.9 kg |  |  | 1.6 mg | 4.8 mg
Oral Suspension Only | 7 kg to 7.9 kg |  |  | 1.8 mg | 5.4 mg
Oral Suspension Only | 8 kg to 8.9 kg |  |  | 2.4 mg | 7.2 mg
Oral Suspension Only | 9 kg to 9.9 kg |  |  | 2.8 mg | 8.4 mg
Oral Suspension Only | 10 kg to 11.9 kg |  |  | 3 mg | 9 mg
Oral Suspension Only | 12 kg to 29.9 kg |  | 5 mg |  | 10 mg
Oral Suspension or Tablets | 30 kg to 49.9 kg | 15 mg |  |  | 15 mg
Oral Suspension or Tablets | ≥50 kg | 20 mg |  |  | 20 mg

Dosing of XARELTO was not studied and therefore dosing cannot be reliably determined in the following patient populations. Its use is therefore not recommended in children less than 6 months of age with any of the following:

- Less than 37 weeks of gestation at birth
- Less than 10 days of oral feeding
- Body weight of less than 2.6 kg.

To increase absorption, all doses should be taken with feeding or with food.

Monitor the child's weight and review the dose regularly, especially for children below 12 kg. This is to ensure a therapeutic dose is maintained.

All pediatric patients (except <2 years old with catheter-related thrombosis):Therapy with XARELTO should be continued for at least 3 months in children with thrombosis. Treatment can be extended up to 12 months when clinically necessary. The benefit of continued therapy beyond 3 months should be assessed on an individual basis taking into account the risk for recurrent thrombosis versus the potential risk of bleeding.

Pediatric patients <2 years old with catheter-related thrombosis:Therapy with XARELTO should be continued for at least 1 month in children less than 2 years old with catheter-related thrombosis. Treatment can be extended up to 3 months when clinically necessary. The benefit of continued therapy beyond 1 month should be assessed on an individual basis taking into account the risk for recurrent thrombosis versus the potential risk of bleeding.

Thromboprophylaxis in Pediatric Patients with Congenital Heart Disease after the Fontan Procedure

Table 3: Recommended Dosage for Thromboprophylaxis in Pediatric Patients with Congenital Heart Disease
Dosage Form | Body Weight | 1 mg XARELTO = 1 mL Suspension
Dosage Form | Body Weight | Dosage |  | Total Daily Dose [All doses can be taken with or without food since exposures match that of 10 mg daily dose in adults.]
Dosage Form | Body Weight | Once a Day [Once a day: approximately 24 hours apart; 2 times a day: approximately 12 hours apart.] | 2 Times a Day
Oral Suspension Only | 7 kg to 7.9 kg |  | 1.1 mg | 2.2 mg
Oral Suspension Only | 8 kg to 9.9 kg |  | 1.6 mg | 3.2 mg
Oral Suspension Only | 10 kg to 11.9 kg |  | 1.7 mg | 3.4 mg
Oral Suspension Only | 12 kg to 19.9 kg |  | 2 mg | 4 mg
Oral Suspension Only | 20 kg to 29.9 kg |  | 2.5 mg | 5 mg
Oral Suspension Only | 30 kg to 49.9 kg | 7.5 mg |  | 7.5 mg
Oral Suspension or Tablets | ≥50 kg | 10 mg |  | 10 mg

Administration in Pediatric Patients

Food Effect:

For the treatment of VTE in children, the dose should be taken with food to increase absorption.

For thromboprophylaxis after Fontan procedure, the dose can be taken with or without food.

Vomit or Spit up:If the patient vomits or spits up the dose within 30 minutes after receiving the dose, a new dose should be given. However, if the patient vomits more than 30 minutes after the dose is taken, the dose should not be re-administered and the next dose should be taken as scheduled. If the patient vomits or spits up the dose repeatedly, the caregiver should contact the child's doctor right away.

Tablets:XARELTO tablet must not be split in an attempt to provide a fraction of a tablet dose.

For children unable to swallow 10, 15, or 20 mg whole tablets, XARELTO oral suspension should be used. XARELTO 2.5 mg tablets are not recommended for use in pediatric patients [see Use in Specific Populations (8.4)].

Use in Renal Impairment in Pediatric Patients

Patients 1 Year of Age or Older

- Mild renal impairment (eGFR: 50 to ≤ 80 mL/min/1.73 m ^2): No dose adjustment is required.
- Moderate or severe renal impairment (eGFR: <50 mL/min/1.73 m ^2): avoid use, as limited clinical data are available.

Estimated glomerular filtration rate (eGFR) can be done using the updated Schwartz formula, eGFR (Schwartz) = (0.413 × height in cm)/serum creatinine in mg/dL, if serum creatinine (SCr) is measured by an enzymatic creatinine method that has been calibrated to be traceable to isotope dilution mass spectrometry (IDMS).

If SCr is measured with routine methods that have not been recalibrated to be traceable to IDMS (e.g., the traditional Jaffé reaction), the eGFR should be obtained from the original Schwartz formula: eGFR (mL/min/1.73 m ^2) = k * height (cm)/SCr (mg/dL), where k is proportionality constant:

- k = 0.55 in children 1 year to 13 years
- k = 0.55 in girls > 13 and < 18 years
- k = 0.70 in boys > 13 and < 18 years

Patients Less than 1 Year of Age

Determine renal function using serum creatinine. Avoid use of XARELTO in pediatric patients younger than 1 year with serum creatinine results above 97.5 th percentile, as no clinical data are available.

Table 4: Reference Values of Serum Creatinine in Pediatric Patients <1 Year of Age
Age | 97.5 th Percentile of Creatinine (mg/dL) | 97.5 th Percentile of Creatinine (µmol/L)
Week 2 | 0.52 | 46
Week 3 | 0.46 | 41
Week 4 | 0.42 | 37
Month 2 | 0.37 | 33
Month 3 | 0.34 | 30
Month 4–6 | 0.34 | 30
Month 7–9 | 0.34 | 30
Month 10–12 | 0.36 | 32

2.3 Switching to and from XARELTO

Switching from Warfarin to XARELTO- When switching patients from warfarin to XARELTO, discontinue warfarin and start XARELTO as soon as the International Normalized Ratio (INR) is below 3.0 in adults and below 2.5 in pediatric patients to avoid periods of inadequate anticoagulation.

Switching from XARELTO to Warfarin –

- Adults:

No clinical trial data are available to guide converting patients from XARELTO to warfarin. XARELTO affects INR, so INR measurements made during coadministration with warfarin may not be useful for determining the appropriate dose of warfarin. One approach is to discontinue XARELTO and begin both a parenteral anticoagulant and warfarin at the time the next dose of XARELTO would have been taken.

- Pediatric Patients:

To ensure adequate anticoagulation during the transition from XARELTO to warfarin, continue XARELTO for at least 2 days after the first dose of warfarin. After 2 days of co-administration, an INR should be obtained prior to the next scheduled dose of XARELTO. Co-administration of XARELTO and warfarin is advised to continue until the INR is ≥ 2.0.

Once XARELTO is discontinued, INR testing may be done reliably 24 hours after the last dose.

Switching from XARELTO to Anticoagulants other than Warfarin- For adult and pediatric patients currently taking XARELTO and transitioning to an anticoagulant with rapid onset, discontinue XARELTO and give the first dose of the other anticoagulant (oral or parenteral) at the time that the next XARELTO dose would have been taken [see Drug Interactions (7.4)].

Switching from Anticoagulants other than Warfarin to XARELTO -For adult and pediatric patients currently receiving an anticoagulant other than warfarin, start XARELTO 0 to 2 hours prior to the next scheduled administration of the drug (e.g., low molecular weight heparin or non-warfarin oral anticoagulant) and omit administration of the other anticoagulant. For unfractionated heparin being administered by continuous infusion, stop the infusion and start XARELTO at the same time.

2.4 Discontinuation for Surgery and other Interventions

If anticoagulation must be discontinued to reduce the risk of bleeding with surgical or other procedures, XARELTO should be stopped at least 24 hours before the procedure to reduce the risk of bleeding [see Warnings and Precautions (5.2)]. In deciding whether a procedure should be delayed until 24 hours after the last dose of XARELTO, the increased risk of bleeding should be weighed against the urgency of intervention. XARELTO should be restarted after the surgical or other procedures as soon as adequate hemostasis has been established, noting that the time to onset of therapeutic effect is short [see Warnings and Precautions (5.1)]. If oral medication cannot be taken during or after surgical intervention, consider administering a parenteral anticoagulant.

2.5 Missed Dose

Adults

- For patients receiving 2.5 mg twice daily: if a dose is missed, the patient should take a single 2.5 mg XARELTO dose as recommended at the next scheduled time.
- For patients receiving 15 mg twice daily: The patient should take XARELTO immediately to ensure intake of 30 mg XARELTO per day. Two 15 mg tablets may be taken at once.
- For patients receiving 20 mg, 15 mg or 10 mg once daily: The patient should take the missed XARELTO dose immediately. The dose should not be doubled within the same day to make up for a missed dose.

Pediatric Patients

- If XARELTO is taken once a day, the patient should take the missed dose as soon as possible once it is noticed, but only on the same day. If this is not possible, the patient should skip the dose and continue with the next dose as prescribed. The patient should not take two doses to make up for a missed dose.
- If XARELTO is taken two times a day, the patient should take the missed morning dose as soon as possible once it is noticed. A missed morning dose may be taken together with the evening dose. A missed evening dose can only be taken in the same evening.
- If XARELTO is taken three times a day, if a dose is missed, the patient should skip the missed dose and go back to the regular dosing schedule at the usual time without compensating for the missed dose.

On the following day, the patient should continue with their regular regimen.

2.6 Administration Options

For adult patients who are unable to swallow whole tablets, XARELTO tablets (all strengths) may be crushed and mixed with applesauce immediately prior to use and administered orally. After the administration of a crushed XARELTO 15 mg or 20 mg tablet, the dose should be immediately followed by food. Administration with food is not required for the 2.5 mg or 10 mg tablets [see Clinical Pharmacology (12.3)].

Administrationof XARELTO tablets via nasogastric (NG) tube or gastric feeding tube:After confirming gastric placement of the tube, XARELTO tablets (all strengths) may be crushed and suspended in 50 mL of water and administered via an NG tube or gastric feeding tube. Since rivaroxaban absorption is dependent on the site of drug release, avoid administration of XARELTO distal to the stomach which can result in reduced absorption and thereby, reduced drug exposure. After the administration of a crushed XARELTO 15 mg or 20 mg tablet, the dose should then be immediately followed by enteral feeding. Enteral feeding is not required following administration of the 2.5 mg or 10 mg tablets [see Clinical Pharmacology (12.3)].

Crushed XARELTO tablets (all strengths) are stable in water and in applesauce for up to 4 hours. An in vitro compatibility study indicated that there is no adsorption of rivaroxaban from a water suspension of a crushed XARELTO tablet to PVC or silicone nasogastric (NG) tubing.

Administration of XARELTO suspension via NG tube or gastric feeding tube: XARELTO oral suspension may be given through NG or gastric feeding tube. After the administration, flush the feeding tube with water.

For the treatment or reduction in risk of recurrent VTE in pediatric patients, the dose should then be immediately followed by enteral feeding to increase absorption. For the thromboprophylaxis in pediatric patients with congenital heart disease who have undergone the Fontan procedure, the dose does not require to be followed by enteral feeding.

An in vitro compatibility study indicated that XARELTO suspension can be used with PVC, polyurethane or silicone NG tubing.

2.7 Preparation Instructions for Pharmacy of XARELTO for Oral Suspension

Do not add flavor as product is already flavored (sweet and creamy).

Reconstitute before dispensing:

- Tap the bottle until all granules flow freely.
- Add 150 mL of purified water for reconstitution.
- Shake for 60 seconds. Check that all granules are wetted and the suspension is uniform.
- Push the adaptor into bottleneck and recap bottle.
- The suspension must be used within 60 days.
- Write the "Discard after" date on the bottle and carton.

Dispensing Instructions:

- Dispense in the original bottle.
- Dispense the bottle upright with the syringes provided in the original carton.

Store reconstituted suspension at room temperature between 20 °C to 25 °C (68 °F to 77 °F); excursions permitted between 15 °C to 30 °C (59 °F to 86 °F). Do not freeze.

It is recommended the pharmacist counsel the caregiver on proper use. Alert the patient or caregiver to read the Medication Guide and Instructions for Use.

3 DOSAGE FORMS AND STRENGTHS

- 2.5 mg tablets: Round, light yellow, and film-coated with a triangle pointing down above a "2.5" marked on one side and "Xa" on the other side
- 10 mg tablets: Round, light red, biconvex and film-coated with a triangle pointing down above a "10" marked on one side and "Xa" on the other side
- 15 mg tablets: Round, red, biconvex, and film-coated with a triangle pointing down above a "15" marked on one side and "Xa" on the other side
- 20 mg tablets: Triangle-shaped, dark red, and film-coated with a triangle pointing down above a "20" marked on one side and "Xa" on the other side
- For oral suspension: white to off-white granules; once reconstituted, provide flavored white to off-white opaque liquid with a concentration of 1 mg/mL.

4 CONTRAINDICATIONS

XARELTO is contraindicated in patients with:

- active pathological bleeding [see Warnings and Precautions (5.2)]
- severe hypersensitivity reaction to XARELTO (e.g., anaphylactic reactions) [see Adverse Reactions (6.2)]

5 WARNINGS AND PRECAUTIONS

5.1 Increased Risk of Thrombotic Events after Premature Discontinuation

Premature discontinuation of any oral anticoagulant, including XARELTO, in the absence of adequate alternative anticoagulation increases the risk of thrombotic events. An increased rate of stroke was observed during the transition from XARELTO to warfarin in clinical trials in atrial fibrillation patients. If XARELTO is discontinued for a reason other than pathological bleeding or completion of a course of therapy, consider coverage with another anticoagulant [see Dosage and Administration (2.3, 2.4) and Clinical Studies (14.1)].

5.2 Risk of Bleeding

XARELTO increases the risk of bleeding, including in any organ, and can cause serious or fatal bleeding. In deciding whether to prescribe XARELTO to patients at increased risk of bleeding, the risk of thrombotic events should be weighed against the risk of bleeding.

Promptly evaluate any signs or symptoms of blood loss and consider the need for blood replacement. Discontinue XARELTO in patients with active pathological hemorrhage. The terminal elimination half-life of rivaroxaban is 5 to 9 hours in healthy subjects aged 20 to 45 years.

Concomitant use of other drugs that impair hemostasis increases the risk of bleeding. These include aspirin, P2Y 12platelet inhibitors, dual antiplatelet therapy, other antithrombotic agents, fibrinolytic therapy, non-steroidal anti-inflammatory drugs (NSAIDs) [see Drug Interactions (7.4)], selective serotonin reuptake inhibitors, and serotonin norepinephrine reuptake inhibitors.

Concomitant use of drugs that are known combined P-gp and strong CYP3A inhibitors increases rivaroxaban exposure and may increase bleeding risk [see Drug Interactions (7.2)].

Risk of Hemorrhage in Acutely Ill Medical Patients at High Risk of Bleeding

Acutely ill medical patients with the following conditions are at increased risk of bleeding with the use of XARELTO for primary VTE prophylaxis: history of bronchiectasis, pulmonary cavitation, or pulmonary hemorrhage, active cancer (i.e., undergoing acute, in-hospital cancer treatment), active gastroduodenal ulcer in the three months prior to treatment, history of bleeding in the three months prior to treatment, or dual antiplatelet therapy. XARELTO is not for use for primary VTE prophylaxis in these hospitalized, acutely ill medical patients at high risk of bleeding.

Reversal of Anticoagulant Effect

An agent to reverse the anti-factor Xa activity of rivaroxaban is available. Because of high plasma protein binding, rivaroxaban is not dialyzable [see Clinical Pharmacology (12.3)]. Protamine sulfate and vitamin K are not expected to affect the anticoagulant activity of rivaroxaban. Use of procoagulant reversal agents, such as prothrombin complex concentrate (PCC), activated prothrombin complex concentrate or recombinant factor VIIa, may be considered but has not been evaluated in clinical efficacy and safety studies. Monitoring for the anticoagulation effect of rivaroxaban using a clotting test (PT, INR or aPTT) or anti-factor Xa (FXa) activity is not recommended.

5.3 Spinal/Epidural Anesthesia or Puncture

When neuraxial anesthesia (spinal/epidural anesthesia) or spinal puncture is employed, patients treated with anticoagulant agents for prevention of thromboembolic complications are at risk of developing an epidural or spinal hematoma which can result in long-term or permanent paralysis [see Boxed Warning].

To reduce the potential risk of bleeding associated with the concurrent use of XARELTO and epidural or spinal anesthesia/analgesia or spinal puncture, consider the pharmacokinetic profile of XARELTO [see Clinical Pharmacology (12.3)]. Placement or removal of an epidural catheter or lumbar puncture is best performed when the anticoagulant effect of XARELTO is low; however, the exact timing to reach a sufficiently low anticoagulant effect in each patient is not known.

An indwelling epidural or intrathecal catheter should not be removed before at least 2 half-lives have elapsed (i.e., 18 hours in young patients aged 20 to 45 years and 26 hours in elderly patients aged 60 to 76 years), after the last administration of XARELTO [see Clinical Pharmacology (12.3)]. The next XARELTO dose should not be administered earlier than 6 hours after the removal of the catheter. If traumatic puncture occurs, delay the administration of XARELTO for 24 hours.

Should the physician decide to administer anticoagulation in the context of epidural or spinal anesthesia/analgesia or lumbar puncture, monitor frequently to detect any signs or symptoms of neurological impairment, such as midline back pain, sensory and motor deficits (numbness, tingling, or weakness in lower limbs), bowel and/or bladder dysfunction. Instruct patients to immediately report if they experience any of the above signs or symptoms. If signs or symptoms of spinal hematoma are suspected, initiate urgent diagnosis and treatment including consideration for spinal cord decompression even though such treatment may not prevent or reverse neurological sequelae.

5.4 Use in Patients with Renal Impairment

Nonvalvular Atrial Fibrillation

Periodically assess renal function as clinically indicated (i.e., more frequently in situations in which renal function may decline) and adjust therapy accordingly [see Dosage and Administration (2.1)]. Consider dose adjustment or discontinuation of XARELTO in patients who develop acute renal failure while on XARELTO [see Use in Specific Populations (8.6)].

Treatment of Deep Vein Thrombosis (DVT), Pulmonary Embolism (PE), and Reduction in the Risk of Recurrence of DVT and of PE

In patients with CrCl <30 mL/min, rivaroxaban exposure and pharmacodynamic effects are increased compared to patients with normal renal function. There are limited clinical data in patients with CrCl 15 to <30 mL/min; therefore, observe closely and promptly evaluate any signs or symptoms of blood loss in these patients. There are no clinical data in patients with CrCl <15 mL/min (including patients on dialysis); therefore, avoid the use of XARELTO in these patients.

Discontinue XARELTO in patients who develop acute renal failure while on treatment [see Use in Specific Populations (8.6)].

Prophylaxis of Deep Vein Thrombosis Following Hip or Knee Replacement Surgery

In patients with CrCl <30 mL/min, rivaroxaban exposure and pharmacodynamic effects are increased compared to patients with normal renal function. There are limited clinical data in patients with CrCl 15 to <30 mL/min; therefore, observe closely and promptly evaluate any signs or symptoms of blood loss in these patients. There are no clinical data in patients with CrCl <15 mL/min (including patients on dialysis); therefore, avoid the use of XARELTO in these patients.

Discontinue XARELTO in patients who develop acute renal failure while on treatment [see Use in Specific Populations (8.6)].

Prophylaxis of Venous Thromboembolism in Acutely Ill Medical Patients at Risk for Thromboembolic Complications Not at High Risk of Bleeding

In patients with CrCl <30 mL/min, rivaroxaban exposure and pharmacodynamic effects are increased compared to patients with normal renal function. There are limited clinical data in patients with CrCl 15 to <30 mL/min; therefore, observe closely and promptly evaluate any signs or symptoms of blood loss in these patients. There are no clinical data in patients with CrCl <15 mL/min (including patients on dialysis); therefore, avoid the use of XARELTO in these patients.

Discontinue XARELTO in patients who develop acute renal failure while on treatment [see Use in Specific Populations (8.6)].

Pediatric Patients

There are limited clinical data in pediatric patients 1 year or older with moderate or severe renal impairment (eGFR <50 mL/min/1.73 m ^2); therefore, avoid the use of XARELTO in these patients.

There are no clinical data in pediatric patients younger than 1 year with serum creatinine results above 97.5 thpercentile; therefore, avoid the use of XARELTO in these patients [see Dosage and Administration (2.2)and Use in Specific Populations (8.6)].

5.5 Use in Patients with Hepatic Impairment

No clinical data are available for adult patients with severe hepatic impairment.

Avoid use of XARELTO in patients with moderate (Child-Pugh B) and severe (Child-Pugh C) hepatic impairment or with any hepatic disease associated with coagulopathy since drug exposure and bleeding risk may be increased [see Use in Specific Populations (8.7)].

No clinical data are available in pediatric patients with hepatic impairment.

5.6 Use with P-gp and Strong CYP3A Inhibitors or Inducers

Avoid concomitant use of XARELTO with known combined P-gp and strong CYP3A inhibitors [see Drug Interactions (7.2)].

Avoid concomitant use of XARELTO with drugs that are known combined P-gp and strong CYP3A inducers [see Drug Interactions (7.3)].

5.7 Risk of Pregnancy-Related Hemorrhage

In pregnant women, XARELTO should be used only if the potential benefit justifies the potential risk to the mother and fetus. XARELTO dosing in pregnancy has not been studied. The anticoagulant effect of XARELTO cannot be monitored with standard laboratory testing. Promptly evaluate any signs or symptoms suggesting blood loss (e.g., a drop in hemoglobin and/or hematocrit, hypotension, or fetal distress) [see Warnings and Precautions (5.2) and Use in Specific Populations (8.1)].

5.8 Patients with Prosthetic Heart Valves

On the basis of the GALILEO study, use of XARELTO is not recommended in patients who have had transcatheter aortic valve replacement (TAVR) because patients randomized to XARELTO experienced higher rates of death and bleeding compared to those randomized to an anti-platelet regimen. The safety and efficacy of XARELTO have not been studied in patients with other prosthetic heart valves or other valve procedures. Use of XARELTO is not recommended in patients with prosthetic heart valves.

5.9 Acute PE in Hemodynamically Unstable Patients or Patients Who Require Thrombolysis or Pulmonary Embolectomy

Initiation of XARELTO is not recommended acutely as an alternative to unfractionated heparin in patients with pulmonary embolism who present with hemodynamic instability or who may receive thrombolysis or pulmonary embolectomy.

5.10 Increased Risk of Thrombosis in Patients with Triple Positive Antiphospholipid Syndrome

Direct-acting oral anticoagulants (DOACs), including XARELTO, are not recommended for use in patients with triple-positive antiphospholipid syndrome (APS). For patients with APS (especially those who are triple positive [positive for lupus anticoagulant, anticardiolipin, and anti-beta 2-glycoprotein I antibodies]), treatment with DOACs has been associated with increased rates of recurrent thrombotic events compared with vitamin K antagonist therapy.

6 ADVERSE REACTIONS

The following clinically significant adverse reactions are also discussed in other sections of the labeling:

- Increased Risk of Stroke After Discontinuation in Nonvalvular Atrial Fibrillation [see Boxed Warningand Warnings and Precautions (5.1)]
- Bleeding Risk [see Warnings and Precautions (5.2, 5.4, 5.5, 5.6, 5.7)]
- Spinal/Epidural Hematoma [see Boxed Warningand Warnings and Precautions (5.3)]

6.1 Clinical Trials Experience

Because clinical trials are conducted under widely varying conditions, adverse reaction rates observed in the clinical trials of a drug cannot be directly compared to rates in the clinical trials of another drug and may not reflect the rates observed in clinical practice.

During clinical development for the approved indications, 34,947 adult patients were exposed to XARELTO.

Hemorrhage

The most common adverse reactions with XARELTO were bleeding complications [see Warnings and Precautions (5.2)].

Nonvalvular Atrial Fibrillation

In the ROCKET AF trial, the most frequent adverse reactions associated with permanent drug discontinuation were bleeding events, with incidence rates of 4.3% for XARELTO vs. 3.1% for warfarin. The incidence of discontinuations for non-bleeding adverse events was similar in both treatment groups.

Table 5 shows the number of patients experiencing various types of bleeding events in the ROCKET AF trial.

Table 5: Bleeding Events in ROCKET AF [Major bleeding events within each subcategory were counted once per patient, but patients may have contributed events to multiple subcategories. These events occurred during treatment or within 2 days of stopping treatment.] - On Treatment Plus 2 Days
Parameter | XARELTO N=7111 n (%/year) | Warfarin N=7125 n (%/year) | XARELTO vs. Warfarin HR (95% CI)
Major Bleeding [Defined as clinically overt bleeding associated with a decrease in hemoglobin of ≥2 g/dL, a transfusion of ≥2 units of packed red blood cells or whole blood, bleeding at a critical site, or with a fatal outcome.] | 395 (3.6) | 386 (3.5) | 1.04 (0.90, 1.20)
Intracranial Hemorrhage (ICH) [Intracranial bleeding events included intraparenchymal, intraventricular, subdural, subarachnoid and/or epidural hematoma.] | 55 (0.5) | 84 (0.7) | 0.67 (0.47, 0.93)
Hemorrhagic Stroke [Hemorrhagic stroke in this table specifically refers to non-traumatic intraparenchymal and/or intraventricular hematoma in patients on treatment plus 2 days.] | 36 (0.3) | 58 (0.5) | 0.63 (0.42, 0.96)
Other ICH | 19 (0.2) | 26 (0.2) | 0.74 (0.41, 1.34)
Gastrointestinal (GI) [Gastrointestinal bleeding events included upper GI, lower GI, and rectal bleeding.] | 221 (2.0) | 140 (1.2) | 1.61 (1.30, 1.99)
Fatal Bleeding [Fatal bleeding is adjudicated death with the primary cause of death from bleeding.] | 27 (0.2) | 55 (0.5) | 0.50 (0.31, 0.79)
ICH | 24 (0.2) | 42 (0.4) | 0.58 (0.35, 0.96)
Non-intracranial | 3 (0.0) | 13 (0.1) | 0.23 (0.07, 0.82)
Abbreviations: HR = Hazard Ratio, CI = Confidence interval, CRNM = Clinically Relevant Non-Major.

Figure 1 shows the risk of major bleeding events across major subgroups.

Figure 1: Risk of Major Bleeding Events by Baseline Characteristics in ROCKET AF – On Treatment Plus 2 Days

Note: The figure above presents effects in various subgroups all of which are baseline characteristics and all of which were pre-specified (diabetic status was not pre-specified in the subgroup but was a criterion for the CHADS2 score). The 95% confidence limits that are shown do not take into account how many comparisons were made, nor do they reflect the effect of a particular factor after adjustment for all other factors. Apparent homogeneity or heterogeneity among groups should not be over-interpreted.

Treatment of Deep Vein Thrombosis (DVT) and/or Pulmonary Embolism (PE)

EINSTEIN DVT and EINSTEIN PE Studies

In the pooled analysis of the EINSTEIN DVT and EINSTEIN PE clinical studies, the most frequent adverse reactions leading to permanent drug discontinuation were bleeding events, with XARELTO vs. enoxaparin/Vitamin K antagonist (VKA) incidence rates of 1.7% vs. 1.5%, respectively. The mean duration of treatment was 208 days for XARELTO-treated patients and 204 days for enoxaparin/VKA-treated patients.

Table 6 shows the number of patients experiencing major bleeding events in the pooled analysis of the EINSTEIN DVT and EINSTEIN PE studies.

Table 6: Bleeding Events [Bleeding event occurred after randomization and up to 2 days after the last dose of study drug. Although a patient may have had 2 or more events, the patient is counted only once in a category.] in the Pooled Analysis of EINSTEIN DVT and EINSTEIN PE Studies
Parameter | XARELTO [Treatment schedule in EINSTEIN DVT and EINSTEIN PE studies: XARELTO 15 mg twice daily for 3 weeks followed by 20 mg once daily; enoxaparin/VKA [enoxaparin: 1 mg/kg twice daily, VKA: individually titrated doses to achieve a target INR of 2.5 (range: 2.0–3.0)]] N=4130 n (%) | Enoxaparin/VKA N=4116 n (%)
Major bleeding event | 40 (1.0) | 72 (1.7)
Fatal bleeding | 3 (<0.1) | 8 (0.2)
Intracranial | 2 (<0.1) | 4 (<0.1)
Non-fatal critical organ bleeding | 10 (0.2) | 29 (0.7)
Intracranial [Treatment-emergent major bleeding events with at least >2 subjects in any pooled treatment group] | 3 (<0.1) | 10 (0.2)
Retroperitoneal | 1 (<0.1) | 8 (0.2)
Intraocular | 3 (<0.1) | 2 (<0.1)
Intra-articular | 0 | 4 (<0.1)
Non-fatal non-critical organ bleeding [Major bleeding which is not fatal or in a critical organ, but resulting in a decrease in Hb ≥ 2 g/dL and/or transfusion of ≥2 units of whole blood or packed red blood cells] | 27 (0.7) | 37 (0.9)
Decrease in Hb ≥ 2 g/dL | 28 (0.7) | 42 (1.0)
Transfusion of ≥2 units of whole blood or packed red blood cells | 18 (0.4) | 25 (0.6)
Clinically relevant non-major bleeding | 357 (8.6) | 357 (8.7)
Any bleeding | 1169 (28.3) | 1153 (28.0)

Reduction in the Risk of Recurrence of DVT and/or PE

EINSTEIN CHOICE Study

In the EINSTEIN CHOICE clinical study, the most frequent adverse reactions associated with permanent drug discontinuation were bleeding events, with incidence rates of 1% for XARELTO 10 mg, 2% for XARELTO 20 mg, and 1% for acetylsalicylic acid (aspirin) 100 mg. The mean duration of treatment was 293 days for XARELTO 10 mg-treated patients and 286 days for aspirin 100 mg-treated patients.

Table 7 shows the number of patients experiencing bleeding events in the EINSTEIN CHOICE study.

Table 7: Bleeding Events [Bleeding event occurred after the first dose and up to 2 days after the last dose of study drug. Although a patient may have had 2 or more events, the patient is counted only once in a category.] in EINSTEIN CHOICE
Parameter | XARELTO [Treatment schedule: XARELTO 10 mg once daily or aspirin 100 mg once daily.] 10 mg N=1127 n (%) | Acetylsalicylic Acid (aspirin) 100 mg N=1131 n (%)
Major bleeding event | 5 (0.4) | 3 (0.3)
Fatal bleeding | 0 | 1 (<0.1)
Non-fatal critical organ bleeding | 2 (0.2) | 1 (<0.1)
Non-fatal non-critical organ bleeding [Major bleeding which is not fatal or in a critical organ, but resulting in a decrease in Hb ≥ 2 g/dL and/or transfusion of ≥ 2 units of whole blood or packed red blood cells.] | 3 (0.3) | 1 (<0.1)
Clinically relevant non-major (CRNM) bleeding [Bleeding which was clinically overt, did not meet the criteria for major bleeding, but was associated with medical intervention, unscheduled contact with a physician, temporary cessation of treatment, discomfort for the patient, or impairment of activities of daily life.] | 22 (2.0) | 20 (1.8)
Any bleeding | 151 (13.4) | 138 (12.2)

In the EINSTEIN CHOICE study, there was an increased incidence of bleeding, including major and CRNM bleeding in the XARELTO 20 mg group compared to the XARELTO 10 mg or aspirin 100 mg groups.

Prophylaxis of Deep Vein Thrombosis Following Hip or Knee Replacement Surgery

In the RECORD clinical trials, the overall incidence rate of adverse reactions leading to permanent treatment discontinuation was 3.7% with XARELTO.

The rates of major bleeding events and any bleeding events observed in patients in the RECORD clinical trials are shown in Table 8.

Table 8: Bleeding Events [Bleeding events occurring any time following the first dose of double-blind study medication (which may have been prior to administration of active drug) until two days after the last dose of double-blind study medication. Patients may have more than one event.] in Patients Undergoing Hip or Knee Replacement Surgeries (RECORD 1–3)
 | XARELTO 10 mg | Enoxaparin [Includes the placebo-controlled period for RECORD 2, enoxaparin dosing was 40 mg once daily (RECORD 1–3)]
Total treated patients | N=4487 n (%) | N=4524 n (%)
Major bleeding event | 14 (0.3) | 9 (0.2)
Fatal bleeding | 1 (<0.1) | 0
Bleeding into a critical organ | 2 (<0.1) | 3 (0.1)
Bleeding that required re-operation | 7 (0.2) | 5 (0.1)
Extra-surgical site bleeding requiring transfusion of >2 units of whole blood or packed cells | 4 (0.1) | 1 (<0.1)
Any bleeding event [Includes major bleeding events] | 261 (5.8) | 251 (5.6)
Hip Surgery Studies | N=3281 n (%) | N=3298 n (%)
Major bleeding event | 7 (0.2) | 3 (0.1)
Fatal bleeding | 1 (<0.1) | 0
Bleeding into a critical organ | 1 (<0.1) | 1 (<0.1)
Bleeding that required re-operation | 2 (0.1) | 1 (<0.1)
Extra-surgical site bleeding requiring transfusion of >2 units of whole blood or packed cells | 3 (0.1) | 1 (<0.1)
Any bleeding event | 201 (6.1) | 191 (5.8)
Knee Surgery Study | N=1206 n (%) | N=1226 n (%)
Major bleeding event | 7 (0.6) | 6 (0.5)
Fatal bleeding | 0 | 0
Bleeding into a critical organ | 1 (0.1) | 2 (0.2)
Bleeding that required re-operation | 5 (0.4) | 4 (0.3)
Extra-surgical site bleeding requiring transfusion of >2 units of whole blood or packed cells | 1 (0.1) | 0
Any bleeding event | 60 (5.0) | 60 (4.9)

Following XARELTO treatment, the majority of major bleeding complications (≥60%) occurred during the first week after surgery.

Prophylaxis of Venous Thromboembolism in Acutely Ill Medical Patients at Risk for Thromboembolic Complications Not at High Risk of Bleeding

In the MAGELLAN study, the most frequent adverse reactions associated with permanent drug discontinuation were bleeding events. Cases of pulmonary hemorrhage and pulmonary hemorrhage with bronchiectasis were observed. Patients with bronchiectasis/pulmonary cavitation, active cancer (i.e., undergoing acute, in-hospital cancer treatment), dual antiplatelet therapy or active gastroduodenal ulcer or any bleeding in the previous three months all had an excess of bleeding with XARELTO compared with enoxaparin/placebo and are excluded from all MAGELLAN data presented in Table 9. The incidence of bleeding leading to drug discontinuation was 2.5% for XARELTO vs. 1.4% for enoxaparin/placebo.

Table 9 shows the number of patients experiencing various types of bleeding events in the MAGELLAN study.

Table 9: Bleeding Events in MAGELLAN [Patients at high risk of bleeding (i.e. bronchiectasis/pulmonary cavitation, active cancer, dual antiplatelet therapy or active gastroduodenal ulcer or any bleeding in the previous three months) were excluded.] Study–Safety Analysis Set - On Treatment Plus 2 Days
MAGELLAN Study [Patients received either XARELTO or placebo once daily for 35 ±4 days starting in hospital and continuing post hospital discharge or received enoxaparin or placebo once daily for 10 ±4 days in the hospital.] | XARELTO 10 mg N=3218 n (%) | Enoxaparin 40 mg /placebo N=3229 n (%)
Major bleeding [Defined as clinically overt bleeding associated with a drop in hemoglobin of ≥2 g/dL, a transfusion of ≥2 units of packed red blood cells or whole blood, bleeding at a critical site, or with a fatal outcome.] [Major bleeding events within each subcategory were counted once per patient, but patients may have contributed events to multiple subcategories. These events occurred during treatment or within 2 days of stopping treatment.] | 22 (0.7) | 15 (0.5)
Critical site bleeding | 7 (0.2) | 4 (0.1)
Fatal bleeding [Fatal bleeding is adjudicated death with the primary cause of death from bleeding.] | 3 (<0.1) | 1 (<0.1)
Clinically relevant non-major bleeding events (CRNM) | 93 (2.9) | 34 (1.1)

Reduction of Risk of Major Cardiovascular Events in Patients with CAD

In the COMPASS trial overall, the most frequent adverse reactions associated with permanent drug discontinuation were bleeding events, with incidence rates of 2.7% for XARELTO 2.5 mg twice daily vs. 1.2% for placebo on background therapy for all patients with aspirin 100 mg once daily. The incidences of important bleeding events in the CAD and PAD populations in COMPASS were similar.

Table 10 shows the number of patients experiencing various types of major bleeding events in the COMPASS trial.

Table 10: Major Bleeding Events in COMPASS - On Treatment Plus 2 Days [Major bleeding events within each subcategory were counted once per patient, but patients may have contributed events to multiple subcategories. These events occurred during treatment or within 2 days of stopping treatment in the safety analysis set in COMPASS patients.]
Parameter | XARELTO [Treatment schedule: XARELTO 2.5 mg twice daily or placebo. All patients received background therapy with aspirin 100 mg once daily.] N=9134 n (%/year) | Placebo N=9107 n (%/year) | XARELTO vs. Placebo HR (95 % CI)
Modified ISTH Major Bleeding [Defined as i) fatal bleeding, or ii) symptomatic bleeding in a critical area or organ, such as intraarticular, intramuscular with compartment syndrome, intraspinal, intracranial, intraocular, respiratory, pericardial, liver, pancreas, retroperitoneal, adrenal gland or kidney; or iii) bleeding into the surgical site requiring reoperation, or iv) bleeding leading to hospitalization.] | 263 (1.6) | 144 (0.9) | 1.8 (1.5, 2.3)
- Fatal bleeding event Intracranial hemorrhage (ICH) Non-intracranial | 12 (<0.1) 6 (<0.1) 6 (<0.1) | 8 (<0.1) 3 (<0.1) 5 (<0.1) | 1.5 (0.6, 3.7) 2.0 (0.5, 8.0) 1.2 (0.4, 4.0)
- Symptomatic bleeding in critical organ (non-fatal) - ICH (fatal and non-fatal) Hemorrhagic Stroke Other ICH | 58 (0.3) 23 (0.1) 18 (0.1) 6 (<0.1) | 43 (0.3) 21 (0.1) 13 (<0.1) 9 (<0.1) | 1.4 (0.9, 2.0) 1.1 (0.6, 2.0) 1.4 (0.7, 2.8) 0.7 (0.2, 1.9)
- Bleeding into the surgical site requiring reoperation (non-fatal, not in critical organ) | 7 (<0.1) | 6 (<0.1) | 1.2 (0.4, 3.5)
- Bleeding leading to hospitalization (non-fatal, not in critical organ, not requiring reoperation) | 188 (1.1) | 91 (0.5) | 2.1 (1.6, 2.7)
Major GI bleeding | 117 (0.7) | 49 (0.3) | 2.4 (1.7, 3.4)
CI: confidence interval; HR: hazard ratio; ISTH: International Society on Thrombosis and Hemostasis

Reduction of Risk of Major Thrombotic Vascular Events in Patients with Peripheral Artery Disease (PAD), Including Patients after Lower Extremity Revascularization due to Symptomatic PAD

The incidence of premature permanent discontinuation due to bleeding events for XARELTO 2.5 mg twice daily vs. placebo on background therapy with aspirin 100 mg once daily in VOYAGER was 4.1% vs. 1.6% and in COMPASS PAD was 2.7% vs. 1.3%, respectively.

Table 11 shows the number of patients experiencing various types of TIMI (Thrombolysis in Myocardial Infarction) major bleeding events in the VOYAGER trial. The most common site of bleeding was gastrointestinal.

Table 11: Major Bleeding Events [Major bleeding events within each subcategory were counted once per patient, but patients may have contributed events to multiple subcategories.] in VOYAGER- On Treatment Plus 2 Days
 | XARELTO [Treatment schedule: XARELTO 2.5 mg twice daily or placebo. All patients received background therapy with aspirin 100 mg once daily.] N=3256 |  | Placebo N=3248 |  | XARELTO vs. Placebo HR (95 % CI)
Parameter | n (%) | Event rate %/year | n (%) | Event rate %/year | XARELTO vs. Placebo HR (95 % CI)
TIMI Major Bleeding (CABG/non-CABG) | 62 (1.9) | 0.96 | 44 (1.4) | 0.67 | 1.4 (1.0, 2.1)
Fatal bleeding | 6 (0.2) | 0.09 | 6 (0.2) | 0.09 | 1.0 (0.3, 3.2)
Intracranial bleeding | 13 (0.4) | 0.20 | 17 (0.5) | 0.26 | 0.8 (0.4, 1.6)
Clinically overt signs of hemorrhage associated with a drop in hemoglobin of ≥5 g/dL or drop in hematocrit of ≥15% | 46 (1.4) | 0.71 | 24 (0.7) | 0.36 | 1.9 (1.2, 3.2)
CABG: Coronary artery bypass graft; CI: confidence interval; HR: hazard ratio; TIMI: Thrombolysis in Myocardial Infarction Bleeding Criteria

Other Adverse Reactions

Non-hemorrhagic adverse reactions reported in ≥1% of XARELTO-treated patients in the EINSTEIN DVT and EINSTEIN PE studies are shown in Table 12.

Table 12: Other Adverse Reactions [Adverse reaction with Relative Risk >1.5 for XARELTO versus comparator] Reported by ≥1% of XARELTO-Treated Patients in EINSTEIN DVT and EINSTEIN PE Studies
Body System Adverse Reaction
EINSTEIN DVT Study | XARELTO 20 mg N=1718 n (%) | Enoxaparin/VKA N=1711 n (%)
Gastrointestinal disorders
Abdominal pain | 46 (2.7) | 25 (1.5)
General disorders and administration site conditions
Fatigue | 24 (1.4) | 15 (0.9)
Musculoskeletal and connective tissue disorders
Back pain | 50 (2.9) | 31 (1.8)
Muscle spasm | 23 (1.3) | 13 (0.8)
Nervous system disorders
Dizziness | 38 (2.2) | 22 (1.3)
Psychiatric disorders
Anxiety | 24 (1.4) | 11 (0.6)
Depression | 20 (1.2) | 10 (0.6)
Insomnia | 28 (1.6) | 18 (1.1)
EINSTEIN PE Study | XARELTO 20 mg N=2412 n (%) | Enoxaparin/VKA N=2405 n (%)
Skin and subcutaneous tissue disorders
Pruritus | 53 (2.2) | 27 (1.1)

Non-hemorrhagic adverse reactions reported in ≥1% of XARELTO-treated patients in RECORD 1–3 studies are shown in Table 13.

Table 13: Other Adverse Drug Reactions [Adverse reaction occurring any time following the first dose of double-blind medication, which may have been prior to administration of active drug, until two days after the last dose of double-blind study medication] Reported by ≥1% of XARELTO-Treated Patients in RECORD 1–3 Studies
Body System Adverse Reaction | XARELTO 10 mg N=4487 n (%) | Enoxaparin [Includes the placebo-controlled period of RECORD 2, enoxaparin dosing was 40 mg once daily (RECORD 1–3)] N=4524 n (%)
Injury, poisoning and procedural complications
Wound secretion | 125 (2.8) | 89 (2.0)
Musculoskeletal and connective tissue disorders
Pain in extremity | 74 (1.7) | 55 (1.2)
Muscle spasm | 52 (1.2) | 32 (0.7)
Nervous system disorders
Syncope | 55 (1.2) | 32 (0.7)
Skin and subcutaneous tissue disorders
Pruritus | 96 (2.1) | 79 (1.8)
Blister | 63 (1.4) | 40 (0.9)

Pediatric Patients

Treatment of Venous Thromboembolism and Reduction in Risk of Recurrent Venous Thromboembolism in Pediatric Patients

The safety assessment is based on data from the EINSTEIN Junior Phase 3 study in 491 patients from birth to less than 18 years of age. Patients were randomized 2:1 to receive body weight-adjusted doses of XARELTO or comparator (unfractionated heparin, low molecular weight heparin, fondaparinux or VKA).

Discontinuation due to bleeding events occurred in 6 (1.8%) patients in the XARELTO group and 3 (1.9%) patients in the comparator group.

Table 14 shows the number of patients experiencing bleeding events in the EINSTEIN Junior study. In female patients who had experienced menarche, ages 12 to <18 years of age, menorrhagia occurred in 23 (27%) female patients in the XARELTO group and 5 (10%) female patients in the comparator group.

Table 14: Bleeding Events in EINSTEIN Junior Study – Safety Analysis Set - Main Treatment Period [These events occurred after randomization until 3 months of treatment (1 month for patients <2 years with central venous catheter-related VTE (CVC-VTE). Patients may have more than one event.]
Parameter | XARELTO [Treatment schedule: body weight-adjusted doses of XARELTO; randomized 2:1 (XARELTO: Comparator).] N=329 n (%) | Comparator Group [Unfractionated heparin (UFH), low molecular weight heparin (LMWH), fondaparinux or VKA.] N=162 n (%)
Major bleeding [Defined as clinically overt bleeding associated with a decrease in hemoglobin of ≥2 g/dL, a transfusion of ≥2 units of packed red blood cells or whole blood, bleeding at a critical site, or with a fatal outcome.] | 0 | 2 (1.2)
Clinically relevant non-major bleeding [Defined as clinically overt bleeding, which did not meet the criteria for major bleeding, but was associated with medical intervention, unscheduled contact with a physician, temporary cessation of treatment, discomfort for the patient, or impairment of activities of daily life.] | 10 (3.0) | 1 (0.6)
Trivial bleeding | 113 (34.3) | 44 (27.2)
Any bleeding | 119 (36.2) | 45 (27.8)

Non-bleeding adverse reactions reported in ≥5% of XARELTO-treated patients are shown in Table 15.

Table 15: Other Adverse Reactions [Adverse reaction with Relative Risk >1.5 for XARELTO versus comparator.] Reported in XARELTO-Treated Patients by ≥5% in EINSTEIN Junior Study
Adverse Reaction | XARELTO N=329 n (%) | Comparator Group N=162 n (%)
Pain in extremity | 23 (7) | 7 (4.3)
Fatigue [The following terms were combined: fatigue, asthenia.] | 23 (7) | 7 (4.3)

A clinically relevant adverse reaction in XARELTO-treated patients was vomiting (10.6% in the XARELTO group vs 8% in the comparator group).

Thromboprophylaxis in Pediatric Patients with Congenital Heart Disease (CHD) after the Fontan Procedure

The data below are based on Part B of the UNIVERSE study which was designed to evaluate the safety and efficacy of XARELTO for thromboprophylaxis in 98 children with CHD after the Fontan procedure who took at least one dose of study drug. Patients in Part B were randomized 2:1 to receive either body weight-adjusted doses of XARELTO or aspirin (approximately 5 mg/kg).

Discontinuation due to bleeding events occurred in 1 (1.6%) patient in the XARELTO group and no patients in the aspirin group.

Table 16 shows the number of patients experiencing bleeding events in the UNIVERSE study.

Table 16: Bleeding Events in UNIVERSE Study - Safety Analysis Set - On Treatment Plus 2 Days
Parameter | XARELTO [Treatment schedule: body weight-adjusted doses of XARELTO or aspirin (approximately 5 mg/kg); randomized 2:1 (XARELTO: Aspirin).] N=64 n (%) | Aspirin N=34 n (%)
Major Bleeding [Defined as clinically overt bleeding associated with a decrease in hemoglobin of ≥2 g/dL, a transfusion of the equivalent of ≥2 units of packed red blood cells or whole blood, bleeding at a critical site, or with a fatal outcome.] | 1 (1.6) | 0
Epistaxis leading to transfusion | 1 (1.6) | 0
Clinically relevant non-major (CRNM) bleeding [Defined as clinically overt bleeding, which did not meet the criteria for major bleeding, but was associated with medical intervention, unscheduled contact with a physician, temporary cessation of treatment, discomfort for the patient, or impairment of activities of daily life.] | 4 (6.3) | 3 (8.8)
Trivial bleeding | 21 (32.8) | 12 (35.3)
Any bleeding | 23 (35.9) | 14 (41.2)

Non-bleeding adverse reactions reported in ≥5% of XARELTO-treated patients are shown in Table 17.

Table 17: Other Adverse Reactions [Adverse reaction with Relative Risk >1.5 for XARELTO versus aspirin.] Reported by ≥5% of XARELTO-Treated Patients in UNIVERSE Study (Part B)
Adverse Reaction | XARELTO N=64 n (%) | Aspirin N=34 n (%)
Cough | 10 (15.6) | 3 (8.8)
Vomiting | 9 (14.1) | 3 (8.8)
Gastroenteritis [The following terms were combined: Gastroenteritis: gastroenteritis, gastroenteritis viral Rash: rash, rash maculo-papular, viral rash] | 8 (12.5) | 1 (2.9)
Rash | 6 (9.4) | 2 (5.9)

6.2 Postmarketing Experience

The following adverse reactions have been identified during post-approval use of XARELTO. Because these reactions are reported voluntarily from a population of uncertain size, it is not always possible to reliably estimate their frequency or establish a causal relationship to drug exposure.

Blood and lymphatic system disorders:agranulocytosis, thrombocytopenia

Hepatobiliary disorders:jaundice, cholestasis, hepatitis (including hepatocellular injury)

Immune system disorders:hypersensitivity, anaphylactic reaction, anaphylactic shock, angioedema

Nervous system disorders:hemiparesis

Renal disorders:Anticoagulant-related nephropathy

Respiratory, thoracic and mediastinal disorders:Eosinophilic pneumonia

Skin and subcutaneous tissue disorders:Stevens-Johnson syndrome, drug reaction with eosinophilia and systemic symptoms (DRESS)

Injury, poisoning and procedural complications:Atraumatic splenic rupture

7 DRUG INTERACTIONS

7.1 General Inhibition and Induction Properties

Rivaroxaban is a substrate of CYP3A4/5, CYP2J2, and the P-gp and ATP-binding cassette G2 (ABCG2) transporters. Combined P-gp and strong CYP3A inhibitors increase exposure to rivaroxaban and may increase the risk of bleeding. Combined P-gp and strong CYP3A inducers decrease exposure to rivaroxaban and may increase the risk of thromboembolic events.

7.2 Drugs that Inhibit Cytochrome P450 3A Enzymes and Drug Transport Systems

Interaction with Combined P-gp and Strong CYP3A Inhibitors

Avoid concomitant administration of XARELTO with known combined P-gp and strong CYP3A inhibitors (e.g., ketoconazole and ritonavir) [see Warnings and Precautions (5.6) and Clinical Pharmacology (12.3)].

Although clarithromycin is a combined P-gp and strong CYP3A inhibitor, pharmacokinetic data suggests that no precautions are necessary with concomitant administration with XARELTO as the change in exposure is unlikely to affect the bleeding risk [see Clinical Pharmacology (12.3)].

Interaction with Combined P-gp and Moderate CYP3A Inhibitors in Patients with Renal Impairment

XARELTO should not be used in patients with CrCl 15 to <80 mL/min who are receiving concomitant combined P-gp and moderate CYP3A inhibitors (e.g., erythromycin) unless the potential benefit justifies the potential risk [see Warnings and Precautions (5.4) and Clinical Pharmacology (12.3)].

7.3 Drugs that Induce Cytochrome P450 3A Enzymes and Drug Transport Systems

Avoid concomitant use of XARELTO with drugs that are combined P-gp and strong CYP3A inducers (e.g., carbamazepine, phenytoin, rifampin, St. John's wort) [see Warnings and Precautions (5.6) and Clinical Pharmacology (12.3)].

7.4 Anticoagulants and NSAIDs/Aspirin

Coadministration of enoxaparin, warfarin, aspirin, clopidogrel and chronic NSAID use may increase the risk of bleeding [see Clinical Pharmacology (12.3)].

Avoid concurrent use of XARELTO with other anticoagulants due to increased bleeding risk unless benefit outweighs risk. Promptly evaluate any signs or symptoms of blood loss if patients are treated concomitantly with aspirin, other platelet aggregation inhibitors, or NSAIDs [see Warnings and Precautions (5.2)].

8 USE IN SPECIFIC POPULATIONS

8.1 Pregnancy

Risk Summary

The limited available data on XARELTO in pregnant women are insufficient to inform a drug-associated risk of adverse developmental outcomes. Use XARELTO with caution in pregnant patients because of the potential for pregnancy related hemorrhage and/or emergent delivery. The anticoagulant effect of XARELTO cannot be reliably monitored with standard laboratory testing. Consider the benefits and risks of XARELTO for the mother and possible risks to the fetus when prescribing XARELTO to a pregnant woman [see Warnings and Precautions (5.2, 5.7)].

Adverse outcomes in pregnancy occur regardless of the health of the mother or the use of medications. The estimated background risk of major birth defects and miscarriage for the indicated populations is unknown. In the U.S. general population, the estimated background risk of major birth defects and miscarriage in clinically recognized pregnancies is 2–4% and 15–20%, respectively.

Clinical Considerations

Disease-Associated Maternal and/or Embryo/Fetal Risk

Pregnancy is a risk factor for venous thromboembolism and that risk is increased in women with inherited or acquired thrombophilias. Pregnant women with thromboembolic disease have an increased risk of maternal complications including pre-eclampsia. Maternal thromboembolic disease increases the risk for intrauterine growth restriction, placental abruption and early and late pregnancy loss.

Fetal/Neonatal Adverse Reactions

Based on the pharmacologic activity of Factor Xa inhibitors and the potential to cross the placenta, bleeding may occur at any site in the fetus and/or neonate.

Labor or Delivery

All patients receiving anticoagulants, including pregnant women, are at risk for bleeding and this risk may be increased during labor or delivery [see Warnings and Precautions (5.7)]. The risk of bleeding should be balanced with the risk of thrombotic events when considering the use of XARELTO in this setting.

Data

Human Data

There are no adequate or well-controlled studies of XARELTO in pregnant women, and dosing for pregnant women has not been established. Post-marketing experience is currently insufficient to determine a rivaroxaban-associated risk for major birth defects or miscarriage. In an in vitro placenta perfusion model, unbound rivaroxaban was rapidly transferred across the human placenta.

Animal Data

Rivaroxaban crosses the placenta in animals. Rivaroxaban increased fetal toxicity (increased resorptions, decreased number of live fetuses, and decreased fetal body weight) when pregnant rabbits were given oral doses of ≥10 mg/kg rivaroxaban during the period of organogenesis. This dose corresponds to about 4 times the human exposure of unbound drug, based on AUC comparisons at the highest recommended human dose of 20 mg/day. Fetal body weights decreased when pregnant rats were given oral doses of 120 mg/kg during the period of organogenesis. This dose corresponds to about 14 times the human exposure of unbound drug. In rats, peripartal maternal bleeding and maternal and fetal death occurred at the rivaroxaban dose of 40 mg/kg (about 6 times maximum human exposure of the unbound drug at the human dose of 20 mg/day).

8.2 Lactation

Risk Summary

Rivaroxaban has been detected in human milk. There are insufficient data to determine the effects of rivaroxaban on the breastfed child or on milk production. Rivaroxaban and/or its metabolites were present in the milk of rats. The developmental and health benefits of breastfeeding should be considered along with the mother's clinical need for XARELTO and any potential adverse effects on the breastfed infant from XARELTO or from the underlying maternal condition (see Data).

Data

Animal Data

Following a single oral administration of 3 mg/kg of radioactive [^14C]-rivaroxaban to lactating rats between Day 8 to 10 postpartum, the concentration of total radioactivity was determined in milk samples collected up to 32 hours post-dose. The estimated amount of radioactivity excreted with milk within 32 hours after administration was 2.1% of the maternal dose.

8.3 Females and Males of Reproductive Potential

Females of reproductive potential requiring anticoagulation should discuss pregnancy planning with their physician.

The risk of clinically significant uterine bleeding, potentially requiring gynecological surgical interventions, identified with oral anticoagulants including XARELTO should be assessed in females of reproductive potential and those with abnormal uterine bleeding.

8.4 Pediatric Use

The safety and effectiveness of XARELTO have been established in pediatric patients from birth to less than 18 years for the treatment of VTE and the reduction in risk of recurrent VTE. Use of XARELTO is supported in these age groups by evidence from adequate and well-controlled studies of XARELTO in adults with additional pharmacokinetic, safety and efficacy data from a multicenter, prospective, open-label, active-controlled randomized study in 500 pediatric patients from birth to less than 18 years of age. XARELTO was not studied and therefore dosing cannot be reliably determined or recommended in children less than 6 months who were less than 37 weeks of gestation at birth; had less than 10 days of oral feeding, or had a body weight of less than 2.6 kg [see Dosage and Administration (2.2), Adverse Reactions (6.1), Clinical Pharmacology (12.3) and Clinical Studies (14.8)].

The safety and effectiveness of XARELTO have been established for use in pediatric patients aged 2 years and older with congenital heart disease who have undergone the Fontan procedure. Use of XARELTO is supported in these age groups by evidence from adequate and well-controlled studies of XARELTO in adults with additional data from a multicenter, prospective, open-label, active controlled study in 112 pediatric patients to evaluate the single- and multiple-dose pharmacokinetic properties of XARELTO and the safety and efficacy of XARELTO when used for thromboprophylaxis for 12 months in children with single ventricle physiology who had the Fontan procedure [see Dosage and Administration (2.2), Adverse Reactions (6.1), Clinical Pharmacology (12.3) and Clinical Studies (14.9)].

Clinical studies that evaluated safety, efficacy, pharmacokinetic and pharmacodynamic data support the use of XARELTO 10 mg, 15 mg, and 20 mg tablets in pediatric patients. For the XARELTO 2.5 mg tablets, there are no safety, efficacy, pharmacokinetic and pharmacodynamic data to support the use in pediatric patients. Therefore, XARELTO 2.5 mg tablets are not recommended for use in pediatric patients.

Although not all adverse reactions identified in the adult population have been observed in clinical trials of children and adolescent patients, the same warnings and precautions for adults should be considered for children and adolescents.

8.5 Geriatric Use

Of the total number of adult patients in clinical trials for the approved indications of XARELTO (N=64,943 patients), 64 percent were 65 years and over, with 27 percent 75 years and over. In clinical trials the efficacy of XARELTO in the elderly (65 years or older) was similar to that seen in patients younger than 65 years. Both thrombotic and bleeding event rates were higher in these older patients [see Clinical Pharmacology (12.3) and Clinical Studies (14)].

8.6 Renal Impairment

In pharmacokinetic studies, compared to healthy adult subjects with normal creatinine clearance, rivaroxaban exposure increased by approximately 44 to 64% in adult subjects with renal impairment. Increases in pharmacodynamic effects were also observed [see Clinical Pharmacology (12.3)].

Nonvalvular Atrial Fibrillation

Patients with Chronic Kidney Disease not on Dialysis

In the ROCKET AF trial, patients with CrCl 30 to 50 mL/min were administered XARELTO 15 mg once daily resulting in serum concentrations of rivaroxaban and clinical outcomes similar to those in patients with better renal function administered XARELTO 20 mg once daily. Patients with CrCl <30 mL/min were not studied, but administration of XARELTO 15 mg once daily is expected to result in serum concentrations of rivaroxaban similar to those in patients with moderate renal impairment [see Clinical Pharmacology (12.3)].

Patients with End-Stage Renal Disease on Dialysis

Clinical efficacy and safety studies with XARELTO did not enroll patients with end-stage renal disease (ESRD) on dialysis. In patients with ESRD maintained on intermittent hemodialysis, administration of XARELTO 15 mg once daily will result in concentrations of rivaroxaban and pharmacodynamic activity similar to those observed in the ROCKET AF study [see Clinical Pharmacology (12.2, 12.3)]. It is not known whether these concentrations will lead to similar stroke reduction and bleeding risk in patients with ESRD on dialysis as was seen in ROCKET AF.

Treatment of DVT and/or PE and Reduction in the Risk of Recurrence of DVT and/or PE

In the EINSTEIN trials, patients with CrCl values <30 mL/min at screening were excluded from the studies, but administration of XARELTO is expected to result in serum concentrations of rivaroxaban similar to those in patients with moderate renal impairment (CrCl 30 to <50 mL/min) [see Clinical Pharmacology (12.3)]. Observe closely and promptly evaluate any signs or symptoms of blood loss in patients with CrCl 15 to <30 mL/min. Avoid the use of XARELTO in patients with CrCl <15 mL/min.

Prophylaxis of DVT Following Hip or Knee Replacement Surgery

The combined analysis of the RECORD 1–3 clinical efficacy studies did not show an increase in bleeding risk for patients with CrCl 30 to 50 mL/min and reported a possible increase in total venous thromboemboli in this population. In the RECORD 1–3 trials, patients with CrCl values <30 mL/min at screening were excluded from the studies, but administration of XARELTO 10 mg once daily is expected to result in serum concentrations of rivaroxaban similar to those in patients with moderate renal impairment (CrCl 30 to <50 mL/min) [see Clinical Pharmacology (12.3)].Observe closely and promptly evaluate any signs or symptoms of blood loss in patients with CrCl 15 to <30 mL/min. Avoid the use of XARELTO in patients with CrCl <15 mL/min.

Prophylaxis of Venous Thromboembolism in Acutely Ill Medical Patients at Risk for Thromboembolic Complications Not at High Risk of Bleeding

Patients with CrCl values <30 mL/min at screening were excluded from the MAGELLAN study. In patients with CrCl <30 mL/min a dose of XARELTO 10 mg once daily is expected to result in serum concentrations of rivaroxaban similar to those in patients with moderate renal impairment (CrCl 30 to <50 mL/min) [see Clinical Pharmacology (12.3)]. Observe closely and promptly evaluate any signs or symptoms of blood loss in patients with CrCl 15 to <30 mL/min. Avoid use of XARELTO in patients with CrCl <15 mL/min.

Reduction of Risk of Major Cardiovascular Events in Patients with CAD and Reduction of Risk of Major Thrombotic Vascular Events in Patients with PAD, Including Patients After Recent Lower Extremity Revascularization due to Symptomatic PAD

Patients with Chronic Kidney Disease not on Dialysis

Patients with a CrCl <15 mL/min at screening were excluded from COMPASS and VOYAGER, and limited data are available for patients with a CrCl of 15 to 30 mL/min. In patients with CrCl <30 mL/min, a dose of 2.5 mg XARELTO twice daily is expected to give an exposure similar to that in patients with moderate renal impairment (CrCl 30 to <50 mL/min) [see Clinical Pharmacology (12.3)], whose efficacy and safety outcomes were similar to those with preserved renal function.

Patients with End-Stage Renal Disease on Dialysis

No clinical outcome data is available for the use of XARELTO with aspirin in patients with ESRD on dialysis since these patients were not enrolled in COMPASS or VOYAGER. In patients with ESRD maintained on intermittent hemodialysis, administration of XARELTO 2.5 mg twice daily will result in concentrations of rivaroxaban and pharmacodynamic activity similar to those observed in moderate renal impaired patients in the COMPASS study [see Clinical Pharmacology (12.2, 12.3)] . It is not known whether these concentrations will lead to similar CV risk reduction and bleeding risk in patients with ESRD on dialysis as was seen in COMPASS.

Pediatric Use

No dosage adjustment is required in patients 1 year of age or older with mild renal impairment (eGFR 50 to ≤ 80 mL/min/1.73 m ^2). There are limited clinical data in pediatric patients 1 year or older with moderate or severe renal impairment (eGFR <50 mL/min/1.73 m ^2); therefore, avoid the use of XARELTO in these patients.

There are no clinical data in pediatric patients younger than 1 year with serum creatinine results above 97.5 thpercentile; therefore, avoid the use of XARELTO in these patients [see Dosage and Administration (2.2)].

8.7 Hepatic Impairment

In a pharmacokinetic study, compared to healthy adult subjects with normal liver function, AUC increases of 127% were observed in adult subjects with moderate hepatic impairment (Child-Pugh B).

The safety or PK of XARELTO in patients with severe hepatic impairment (Child-Pugh C) has not been evaluated [see Clinical Pharmacology (12.3)].

Avoid the use of XARELTO in patients with moderate (Child-Pugh B) and severe (Child-Pugh C) hepatic impairment or with any hepatic disease associated with coagulopathy.

No clinical data are available in pediatric patients with hepatic impairment.

10 OVERDOSAGE

Overdose of XARELTO may lead to hemorrhage. Discontinue XARELTO and initiate appropriate therapy if bleeding complications associated with overdosage occur. Rivaroxaban systemic exposure is not further increased at single doses >50 mg due to limited absorption. The use of activated charcoal to reduce absorption in case of XARELTO overdose may be considered. Due to the high plasma protein binding, rivaroxaban is not dialyzable [see Warnings and Precautions (5.2) and Clinical Pharmacology (12.3)]. Partial reversal of laboratory anticoagulation parameters may be achieved with use of plasma products. An agent to reverse the anti-factor Xa activity of rivaroxaban is available.

11 DESCRIPTION

Rivaroxaban, a factor Xa (FXa) inhibitor, is the active ingredient in XARELTO ®Tablets and XARELTO ®for oral suspension with the chemical name 5-Chloro-N-({(5S)-2-oxo-3-[4-(3-oxo-4-morpholinyl)phenyl]-1,3-oxazolidin-5-yl}methyl)-2-thiophenecarboxamide. The molecular formula of rivaroxaban is C 19H 18ClN 3O 5S and the molecular weight is 435.89. The structural formula is:

Rivaroxaban is a pure (S)-enantiomer. It is an odorless, non-hygroscopic, white to yellowish powder. Rivaroxaban is only slightly soluble in organic solvents (e.g., acetone, polyethylene glycol 400) and is practically insoluble in water and aqueous media.

Each XARELTO tablet contains 2.5 mg, 10 mg, 15 mg, or 20 mg of rivaroxaban. The inactive ingredients of XARELTO are: croscarmellose sodium, hypromellose, lactose monohydrate, magnesium stearate, microcrystalline cellulose, and sodium lauryl sulfate. Additionally, the proprietary film coating mixture used for XARELTO 2.5 mg is Opadry® Light Yellow, containing ferric oxide yellow, hypromellose, polyethylene glycol 3350, and titanium dioxide, and for XARELTO 10 mg tablets is Opadry® Pink and for XARELTO 15 mg tablets is Opadry® Red, both containing ferric oxide red, hypromellose, polyethylene glycol 3350, and titanium dioxide, and for XARELTO 20 mg tablets is Opadry® II Dark Red, containing ferric oxide red, polyethylene glycol 3350, polyvinyl alcohol (partially hydrolyzed), talc, and titanium dioxide.

XARELTO for oral suspension is supplied as granules in bottles containing 155 mg of rivaroxaban (1 mg of rivaroxaban per mL after reconstitution). The inactive ingredients are: anhydrous citric acid, hypromellose, mannitol, microcrystalline cellulose and carboxymethylcellulose sodium, sodium benzoate, sucralose, sweet and creamy flavor and xanthan gum.

12 CLINICAL PHARMACOLOGY

12.1 Mechanism of Action

XARELTO is a selective inhibitor of FXa. It does not require a cofactor (such as Anti-thrombin III) for activity. Rivaroxaban inhibits free FXa and prothrombinase activity. Rivaroxaban has no direct effect on platelet aggregation, but indirectly inhibits platelet aggregation induced by thrombin. By inhibiting FXa, rivaroxaban decreases thrombin generation.

12.2 Pharmacodynamics

Rivaroxaban produces dose-dependent inhibition of FXa activity. Clotting tests, such as prothrombin time (PT), activated partial thromboplastin time (aPTT) and HepTest ®, are also prolonged dose-dependently. In children treated with rivaroxaban, the correlation between anti-factor Xa to plasma concentrations is linear with a slope close to 1.

Monitoring for anticoagulation effect of rivaroxaban using anti-FXa activity or a clotting test is not recommended.

Specific Populations

Renal Impairment

The relationship between systemic exposure and pharmacodynamic activity of rivaroxaban was altered in adult subjects with renal impairment relative to healthy control subjects [see Use in Specific Populations (8.6)].

Table 18: Percentage Increase in Rivaroxaban PK and PD Measures in Adult Subjects with Renal Impairment Relative to Healthy Subjects from Clinical Pharmacology Studies
Measure | Parameter | Creatinine Clearance (mL/min)
Measure | Parameter | 50–79 | 30–49 | 15–29 | ESRD (on dialysis) [Separate stand-alone study.] | ESRD (post-dialysis)
Exposure | AUC | 44 | 52 | 64 | 47 | 56
FXa Inhibition | AUEC | 50 | 86 | 100 | 49 | 33
PT Prolongation | AUEC | 33 | 116 | 144 | 112 | 158
PT = Prothrombin time; FXa = Coagulation factor Xa; AUC = Area under the plasma concentration-time curve; AUEC = Area under the effect-time curve

Hepatic Impairment

Anti-Factor Xa activity was similar in adult subjects with normal hepatic function and in mild hepatic impairment (Child-Pugh A class). There is no clear understanding of the impact of hepatic impairment beyond this degree on the coagulation cascade and its relationship to efficacy and safety.

12.3 Pharmacokinetics

Absorption

The absolute bioavailability of rivaroxaban is dose-dependent. For the 2.5 mg and 10 mg dose, it is estimated to be 80% to 100% and is not affected by food. XARELTO 2.5 mg and 10 mg tablets can be taken with or without food. XARELTO 20 mg administered in the fasted state has an absolute bioavailability of approximately 66%. Coadministration of XARELTO with food increases the bioavailability of the 20 mg dose (mean AUC and C max increasing by 39% and 76% respectively with food). XARELTO 15 mg and 20 mg tablets should be taken with food [see Dosage and Administration (2.1)].

The maximum concentrations (C max) of rivaroxaban appear 2 to 4 hours after tablet intake. The pharmacokinetics of rivaroxaban were not affected by drugs altering gastric pH. Coadministration of XARELTO (30 mg single dose) with the H 2-receptor antagonist ranitidine (150 mg twice daily), the antacid aluminum hydroxide/magnesium hydroxide (10 mL) or XARELTO (20 mg single dose) with the PPI omeprazole (40 mg once daily) did not show an effect on the bioavailability and exposure of rivaroxaban (see Figure 3).

Absorption of rivaroxaban is dependent on the site of drug release in the GI tract. A 29% and 56% decrease in AUC and C max compared to tablet was reported when rivaroxaban granulate is released in the proximal small intestine. Exposure is further reduced when drug is released in the distal small intestine, or ascending colon. Avoid administration of rivaroxaban distal to the stomach which can result in reduced absorption and related drug exposure.

In a study with 44 healthy subjects, both mean AUC and C max values for 20 mg rivaroxaban administered orally as a crushed tablet mixed in applesauce were comparable to that after the whole tablet. However, for the crushed tablet suspended in water and administered via an NG tube followed by a liquid meal, only mean AUC was comparable to that after the whole tablet, and C max was 18% lower.

Distribution

Protein binding of rivaroxaban in human plasma is approximately 92% to 95%, with albumin being the main binding component. The steady-state volume of distribution in healthy subjects is approximately 50 L.

Metabolism

Approximately 51% of an orally administered [^14C]-rivaroxaban dose was recovered as inactive metabolites in urine (30%) and feces (21%). Oxidative degradation catalyzed by CYP3A4/5 and CYP2J2 and hydrolysis are the major sites of biotransformation. Unchanged rivaroxaban was the predominant moiety in plasma with no major or active circulating metabolites.

Excretion

In a Phase 1 study, following the administration of [^14C]-rivaroxaban, approximately one-third (36%) was recovered as unchanged drug in the urine and 7% was recovered as unchanged drug in feces. Unchanged drug is excreted into urine, mainly via active tubular secretion and to a lesser extent via glomerular filtration (approximate 5:1 ratio). Rivaroxaban is a substrate of the efflux transporter proteins P-gp and ABCG2 (also abbreviated BCRP). Rivaroxaban's affinity for influx transporter proteins is unknown.

Rivaroxaban is a low-clearance drug, with a systemic clearance of approximately 10 L/hr in healthy volunteers following intravenous administration. The terminal elimination half-life of rivaroxaban is 5 to 9 hours in healthy subjects aged 20 to 45 years.

Specific Populations

The effects of level of renal impairment, age, body weight, and level of hepatic impairment on the pharmacokinetics of rivaroxaban are summarized in Figure 2.

Figure 2: Effect of Specific Adult Populations on the Pharmacokinetics of Rivaroxaban

[see Dosage and Administration (2.1)]

Gender

Gender did not influence the pharmacokinetics or pharmacodynamics of XARELTO.

Race

Healthy Japanese subjects were found to have 20 to 40% on average higher exposures compared to other ethnicities including Chinese. However, these differences in exposure are reduced when values are corrected for body weight.

Hemodialysis in ESRD subjects:Systemic exposure to rivaroxaban administered as a single 15 mg dose in ESRD subjects dosed 3 hours after the completion of a 4-hour hemodialysis session (post-dialysis) is 56% higher when compared to subjects with normal renal function (see Table 18). The systemic exposure to rivaroxaban administered 2 hours prior to a 4-hour hemodialysis session with a dialysate flow rate of 600 mL/min and a blood flow rate in the range of 320 to 400 mL/min is 47% higher compared to those with normal renal function. The extent of the increase is similar to the increase in patients with CrCl 15 to 50 mL/min taking XARELTO 15 mg. Hemodialysis had no significant impact on rivaroxaban exposure. Protein binding was similar (86% to 89%) in healthy controls and ESRD subjects in this study.

Pediatric Patients:Limited clinical data are available in children 1 year or older with moderate or severe renal impairment (eGFR <50 mL/min/1.73 m ^2) or in children younger than 1 year with serum creatinine results above 97.5th percentile [see Dosage and Administration (2.2) and Use in Specific Populations (8.6)].

Elderly

The terminal elimination half-life is 11 to 13 hours in the elderly subjects aged 60 to 76 years [see Use in Specific Populations (8.5)].

Pediatric Patients

The rate and extent of absorption were similar between the tablet and suspension. After repeated administration of rivaroxaban for the treatment of VTE, the C max of rivaroxaban in plasma was observed at median times of 1.5 to 2.2 hours in subjects who ranged from birth to less than 18 years of age.

In children who were 6 months to 9 years of age, in vitro plasma protein binding of rivaroxaban is approximately 90%.

The half-life of rivaroxaban in plasma of pediatric patients treated for VTE decreased with decreasing age. Mean half-life values were 4.2 hours in adolescents, 3 hours in children 2 to 12 years of age, 1.9 hours in children 0.5 to <2 years of age, and 1.6 hours in children <0.5 years of age.

An exploratory analysis in pediatric patients treated for VTE did not reveal relevant differences in rivaroxaban exposure based on gender or race.

Renal Impairment

The safety and pharmacokinetics of single-dose XARELTO (10 mg) were evaluated in a study in healthy subjects [CrCl ≥80 mL/min (n=8)] and in subjects with varying degrees of renal impairment (see Figure 2). Compared to healthy subjects with normal creatinine clearance, rivaroxaban exposure increased in subjects with renal impairment. Increases in pharmacodynamic effects were also observed [see Use in Specific Populations (8.6)].

Hepatic Impairment

The safety and pharmacokinetics of single-dose XARELTO (10 mg) were evaluated in a study in healthy adult subjects (n=16) and adult subjects with varying degrees of hepatic impairment (see Figure 2). No patients with severe hepatic impairment (Child-Pugh C) were studied. Compared to healthy subjects with normal liver function, significant increases in rivaroxaban exposure were observed in subjects with moderate hepatic impairment (Child-Pugh B) (see Figure 2). Increases in pharmacodynamic effects were also observed [see Use in Specific Populations (8.7)].

No clinical data are available in pediatric patients with hepatic impairment.

Drug Interactions

In vitrostudies indicate that rivaroxaban neither inhibits the major cytochrome P450 enzymes CYP1A2, 2C8, 2C9, 2C19, 2D6, 2J2, and 3A nor induces CYP1A2, 2B6, 2C19, or 3A. In vitro data also indicates a low rivaroxaban inhibitory potential for P-gp and ABCG2 transporters.

The effects of coadministered drugs on the pharmacokinetics of rivaroxaban exposure are summarized in Figure 3 [see Drug Interactions (7)].

Figure 3: Effect of Coadministered Drugs on the Pharmacokinetics of Rivaroxaban in Adults

Anticoagulants

In a drug interaction study, single doses of enoxaparin (40 mg subcutaneous) and XARELTO (10 mg) given concomitantly resulted in an additive effect on anti-factor Xa activity. In another study, single doses of warfarin (15 mg) and XARELTO (5 mg) resulted in an additive effect on factor Xa inhibition and PT. Neither enoxaparin nor warfarin affected the pharmacokinetics of rivaroxaban (see Figure 3).

NSAIDs/Aspirin

In ROCKET AF, concomitant aspirin use (almost exclusively at a dose of 100 mg or less) during the double-blind phase was identified as an independent risk factor for major bleeding. NSAIDs are known to increase bleeding, and bleeding risk may be increased when NSAIDs are used concomitantly with XARELTO. Neither naproxen nor aspirin affected the pharmacokinetics of rivaroxaban (see Figure 3).

Clopidogrel

In two drug interaction studies where clopidogrel (300 mg loading dose followed by 75 mg daily maintenance dose) and XARELTO (15 mg single dose) were coadministered in healthy subjects, an increase in bleeding time to 45 minutes was observed in approximately 45% and 30% of subjects in these studies, respectively. The change in bleeding time was approximately twice the maximum increase seen with either drug alone. There was no change in the pharmacokinetics of either drug.

Drug-Disease Interactions with Drugs that Inhibit Cytochrome P450 3A Enzymes and Drug Transport Systems

In a pharmacokinetic trial, XARELTO was administered as a single dose in subjects with mild (CrCl = 50 to 79 mL/min) or moderate renal impairment (CrCl = 30 to 49 mL/min) receiving multiple doses of erythromycin (a combined P-gp and moderate CYP3A inhibitor). Compared to XARELTO administered alone in subjects with normal renal function (CrCl >80 mL/min), subjects with mild and moderate renal impairment concomitantly receiving erythromycin reported a 76% and 99% increase in AUC infand a 56% and 64% increase in C max, respectively. Similar trends in pharmacodynamic effects were also observed.

12.6 QT/QTc Prolongation

In a thorough QT study in healthy men and women aged 50 years and older, no QTc prolonging effects were observed for XARELTO (15 mg and 45 mg, single-dose).

13 NON-CLINICAL TOXICOLOGY

13.1 Carcinogenesis, Mutagenesis, Impairment of Fertility

Rivaroxaban was not carcinogenic when administered by oral gavage to mice or rats for up to 2 years. The systemic exposures (AUCs) of unbound rivaroxaban in male and female mice at the highest dose tested (60 mg/kg/day) were 1- and 2-times, respectively, the human exposure of unbound drug at the human dose of 20 mg/day. Systemic exposures of unbound drug in male and female rats at the highest dose tested (60 mg/kg/day) were 2- and 4-times, respectively, the human exposure.

Rivaroxaban was not mutagenic in bacteria (Ames-Test) or clastogenic in V79 Chinese hamster lung cells in vitro or in the mouse micronucleus test in vivo.

No impairment of fertility was observed in male or female rats when given up to 200 mg/kg/day of rivaroxaban orally. This dose resulted in exposure levels, based on the unbound AUC, at least 13 times the exposure in humans given 20 mg rivaroxaban daily.

14 CLINICAL STUDIES

14.1 Stroke Prevention in Nonvalvular Atrial Fibrillation

The evidence for the efficacy and safety of XARELTO was derived from Rivaroxaban Once-daily oral direct factor Xa inhibition Compared with vitamin Kantagonist for the prevention of stroke an Embolism Trial in Atrial Fibrillation (ROCKET AF) [NCT00403767], a multi-national, double-blind study comparing XARELTO (at a dose of 20 mg once daily with the evening meal in patients with CrCl >50 mL/min and 15 mg once daily with the evening meal in patients with CrCl 30 to 50 mL/min) to warfarin (titrated to INR 2.0 to 3.0) to reduce the risk of stroke and non-central nervous system (CNS) systemic embolism in patients with nonvalvular atrial fibrillation (AF). Patients had to have one or more of the following additional risk factors for stroke:

- a prior stroke (ischemic or unknown type), transient ischemic attack (TIA) or non-CNS systemic embolism, or
- 2 or more of the following risk factors:
  - age ≥75 years,
  - hypertension,
  - heart failure or left ventricular ejection fraction ≤35%, or
  - diabetes mellitus

ROCKET AF was a non-inferiority study designed to demonstrate that XARELTO preserved more than 50% of warfarin's effect on stroke and non-CNS systemic embolism as established by previous placebo-controlled studies of warfarin in atrial fibrillation.

A total of 14264 patients were randomized and followed on study treatment for a median of 590 days. The mean age was 71 years and the mean CHADS 2score was 3.5. The population was 60% male, 83% Caucasian, 13% Asian and 1.3% Black. There was a history of stroke, TIA, or non-CNS systemic embolism in 55% of patients, and 38% of patients had not taken a vitamin K antagonist (VKA) within 6 weeks at time of screening. Concomitant diseases of patients in this study included hypertension 91%, diabetes 40%, congestive heart failure 63%, and prior myocardial infarction 17%. At baseline, 37% of patients were on aspirin (almost exclusively at a dose of 100 mg or less) and few patients were on clopidogrel. Patients were enrolled in Eastern Europe (39%); North America (19%); Asia, Australia, and New Zealand (15%); Western Europe (15%); and Latin America (13%). Patients randomized to warfarin had a mean percentage of time in the INR target range of 2.0 to 3.0 of 55%, lower during the first few months of the study.

In ROCKET AF, XARELTO was demonstrated non-inferior to warfarin for the primary composite endpoint of time to first occurrence of stroke (any type) or non-CNS systemic embolism [HR (95% CI): 0.88 (0.74, 1.03)], but superiority to warfarin was not demonstrated. There is insufficient experience to determine how XARELTO and warfarin compare when warfarin therapy is well-controlled.

Table 19 displays the overall results for the primary composite endpoint and its components.

Table 19: Primary Composite Endpoint Results in ROCKET AF Study (Intent-to-Treat Population)
 | XARELTO |  | Warfarin |  | XARELTO vs. Warfarin
Event | N=7081 n (%) | Event Rate (per 100 Pt-yrs) | N=7090 n (%) | Event Rate (per 100 Pt-yrs) | Hazard Ratio (95% CI)
Primary Composite Endpoint [The primary endpoint was the time to first occurrence of stroke (any type) or non-CNS systemic embolism. Data are shown for all randomized patients followed to site notification that the study would end.] | 269 (3.8) | 2.1 | 306 (4.3) | 2.4 | 0.88 (0.74, 1.03)
Stroke | 253 (3.6) | 2.0 | 281 (4.0) | 2.2
Hemorrhagic Stroke [Defined as primary hemorrhagic strokes confirmed by adjudication in all randomized patients followed up to site notification] | 33 (0.5) | 0.3 | 57 (0.8) | 0.4
Ischemic Stroke | 206 (2.9) | 1.6 | 208 (2.9) | 1.6
Unknown Stroke Type | 19 (0.3) | 0.2 | 18 (0.3) | 0.1
Non-CNS Systemic Embolism | 20 (0.3) | 0.2 | 27 (0.4) | 0.2

Figure 4 is a plot of the time from randomization to the occurrence of the first primary endpoint event in the two treatment arms.

Figure 4: Time to First Occurrence of Stroke (any type) or Non-CNS Systemic Embolism by Treatment Group (Intent-to-Treat Population)

Figure 5 shows the risk of stroke or non-CNS systemic embolism across major subgroups.

Figure 5: Risk of Stroke or Non-CNS Systemic Embolism by Baseline Characteristics in ROCKET AF [Data are shown for all randomized patients followed to site notification that the study would end.] (Intent-to-Treat Population)

Note: The figure above presents effects in various subgroups all of which are baseline characteristics and all of which were pre-specified (diabetic status was not pre-specified in the subgroup, but was a criterion for the CHADS2 score). The 95% confidence limits that are shown do not take into account how many comparisons were made, nor do they reflect the effect of a particular factor after adjustment for all other factors. Apparent homogeneity or heterogeneity among groups should not be over-interpreted.

The efficacy of XARELTO was generally consistent across major subgroups.

The protocol for ROCKET AF did not stipulate anticoagulation after study drug discontinuation, but warfarin patients who completed the study were generally maintained on warfarin. XARELTO patients were generally switched to warfarin without a period of coadministration of warfarin and XARELTO, so that they were not adequately anticoagulated after stopping XARELTO until attaining a therapeutic INR. During the 28 days following the end of the study, there were 22 strokes in the 4637 patients taking XARELTO vs. 6 in the 4691 patients taking warfarin.

Few patients in ROCKET AF underwent electrical cardioversion for atrial fibrillation. The utility of XARELTO for preventing post-cardioversion stroke and systemic embolism is unknown.

14.2 Treatment of Deep Vein Thrombosis (DVT) and/or Pulmonary Embolism (PE)

EINSTEIN Deep Vein Thrombosis and EINSTEIN Pulmonary Embolism Studies

XARELTO for the treatment of DVT and/or PE was studied in EINSTEIN DVT [NCT00440193] and EINSTEIN PE [NCT00439777], multi-national, open-label, non-inferiority studies comparing XARELTO (at an initial dose of 15 mg twice daily with food for the first three weeks, followed by XARELTO 20 mg once daily with food) to enoxaparin 1 mg/kg twice daily for at least five days with VKA and then continued with VKA only after the target INR (2.0–3.0) was reached. Patients who required thrombectomy, insertion of a caval filter, or use of a fibrinolytic agent and patients with creatinine clearance <30 mL/min, significant liver disease, or active bleeding were excluded from the studies. The intended treatment duration was 3, 6, or 12 months based on investigator's assessment prior to randomization.

A total of 8281 (3449 in EINSTEIN DVT and 4832 in EINSTEIN PE) patients were randomized and followed on study treatment for a mean of 208 days in the XARELTO group and 204 days in the enoxaparin/VKA group. The mean age was approximately 57 years. The population was 55% male, 70% Caucasian, 9% Asian and about 3% Black. About 73% and 92% of XARELTO-treated patients in the EINSTEIN DVT and EINSTEIN PE studies, respectively, received initial parenteral anticoagulant treatment for a median duration of 2 days. Enoxaparin/VKA-treated patients in the EINSTEIN DVT and EINSTEIN PE studies received initial parenteral anticoagulant treatment for a median duration of 8 days. Aspirin was taken as on treatment concomitant antithrombotic medication by approximately 12% of patients in both treatment groups. Patients randomized to VKA had an unadjusted mean percentage of time in the INR target range of 2.0 to 3.0 of 58% in EINSTEIN DVT study and 60% in EINSTEIN PE study, with the lower values occurring during the first month of the study.

In the EINSTEIN DVT and EINSTEIN PE studies, 49% of patients had an idiopathic DVT/PE at baseline. Other risk factors included previous episode of DVT/PE (19%), recent surgery or trauma (18%), immobilization (16%), use of estrogen-containing drug (8%), known thrombophilic conditions (6%), or active cancer (5%).

In the EINSTEIN DVT and EINSTEIN PE studies, XARELTO was demonstrated to be non-inferior to enoxaparin/VKA for the primary composite endpoint of time to first occurrence of recurrent DVT or non-fatal or fatal PE [EINSTEIN DVT HR (95% CI): 0.68 (0.44, 1.04); EINSTEIN PE HR (95% CI): 1.12 (0.75, 1.68)]. In each study the conclusion of non-inferiority was based on the upper limit of the 95% confidence interval for the hazard ratio being less than 2.0.

Table 20 displays the overall results for the primary composite endpoint and its components for EINSTEIN DVT and EINSTEIN PE studies.

Table 20: Primary Composite Endpoint Results [For the primary efficacy analysis, all confirmed events were considered from randomization up to the end of intended treatment duration (3, 6 or 12 months) irrespective of the actual treatment duration. If the same patient had several events, the patient may have been counted for several components.] in EINSTEIN DVT and EINSTEIN PE Studies – Intent-to-Treat Population
Event | XARELTO 20 mg [Treatment schedule in EINSTEIN DVT and EINSTEIN PE studies: XARELTO 15 mg twice daily for 3 weeks followed by 20 mg once daily; enoxaparin/VKA [enoxaparin: 1 mg/kg twice daily, VKA: individually titrated doses to achieve a target INR of 2.5 (range: 2.0–3.0)]] | Enoxaparin/VKA | XARELTO vs. Enoxaparin/VKA Hazard Ratio (95% CI)
EINSTEIN DVT Study | N=1731 n (%) | N=1718 n (%)
Primary Composite Endpoint | 36 (2.1) | 51 (3.0) | 0.68 (0.44, 1.04)
Death (PE) | 1 (<0.1) | 0
Death (PE cannot be excluded) | 3 (0.2) | 6 (0.3)
Symptomatic PE and DVT | 1 (<0.1) | 0
Symptomatic recurrent PE only | 20 (1.2) | 18 (1.0)
Symptomatic recurrent DVT only | 14 (0.8) | 28 (1.6)
EINSTEIN PE Study | N=2419 n (%) | N=2413 n (%)
Primary Composite Endpoint | 50 (2.1) | 44 (1.8) | 1.12 (0.75, 1.68)
Death (PE) | 3 (0.1) | 1 (<0.1)
Death (PE cannot be excluded) | 8 (0.3) | 6 (0.2)
Symptomatic PE and DVT | 0 | 2 (<0.1)
Symptomatic recurrent PE only | 23 (1.0) | 20 (0.8)
Symptomatic recurrent DVT only | 18 (0.7) | 17 (0.7)

Figures 6 and 7 are plots of the time from randomization to the occurrence of the first primary efficacy endpoint event in the two treatment groups in EINSTEIN DVT and EINSTEIN PE studies, respectively.

Figure 6: Time to First Occurrence of the Composite of Recurrent DVT or Non-fatal or Fatal PE by Treatment Group (Intent-to-Treat Population) – EINSTEIN DVT Study

Figure 7: Time to First Occurrence of the Composite of Recurrent DVT or Non-fatal or Fatal PE by Treatment Group (Intent-to-Treat Population) – EINSTEIN PE Study

14.3 Reduction in the Risk of Recurrence of DVT and/or PE

EINSTEIN CHOICE Study

XARELTO for reduction in the risk of recurrence of DVT and of PE was evaluated in the EINSTEIN CHOICE study [NCT02064439], a multi-national, double-blind, superiority study comparing XARELTO (10 or 20 mg once daily with food) to 100 mg acetylsalicylic acid (aspirin) once daily in patients who had completed 6 to 12 months of anticoagulant treatment for DVT and/or PE following the acute event. The intended treatment duration in the study was up to 12 months. Patients with an indication for continued therapeutic-dose anticoagulation were excluded.

Because the benefit-risk assessment favored the 10 mg dose versus aspirin compared to the 20 mg dose versus aspirin, only the data concerning the 10 mg dose is discussed below.

A total of 2275 patients were randomized and followed on study treatment for a mean of 290 days for the XARELTO and aspirin treatment groups. The mean age was approximately 59 years. The population was 56% male, 70% Caucasian, 14% Asian and 3% Black. In the EINSTEIN CHOICE study, 51% of patients had DVT only, 33% had PE only, and 16% had PE and DVT combined. Other risk factors included idiopathic VTE (43%), previous episode of DVT/PE (17%), recent surgery or trauma (12%), prolonged immobilization (10%), use of estrogen containing drugs (5%), known thrombophilic conditions (6%), Factor V Leiden gene mutation (4%), or active cancer (3%).

In the EINSTEIN CHOICE study, XARELTO 10 mg was demonstrated to be superior to aspirin 100 mg for the primary composite endpoint of time to first occurrence of recurrent DVT or non-fatal or fatal PE.

Table 21 displays the overall results for the primary composite endpoint and its components.

Table 21: Primary Composite Endpoint and its Components Results [For the primary efficacy analysis, all confirmed events were considered from randomization up to the end of intended treatment duration (12 months) irrespective of the actual treatment duration. The individual component of the primary endpoint represents the first occurrence of the event.] in EINSTEIN CHOICE Study – Full Analysis Set
Event | XARELTO 10 mg N=1,127 n (%) | Acetylsalicylic Acid (Aspirin) 100 mg N=1,131 n (%) | XARELTO 10 mg vs. Aspirin 100 mg Hazard Ratio (95% CI)
Primary Composite Endpoint | 13 (1.2) | 50 (4.4) | 0.26 (0.14, 0.47) p<0.0001
Symptomatic recurrent DVT | 8 (0.7) | 29 (2.6)
Symptomatic recurrent PE | 5 (0.4) | 19 (1.7)
Death (PE) | 0 | 1 (<0.1)
Death (PE cannot be excluded) | 0 | 1 (<0.1)

Figure 8 is a plot of the time from randomization to the occurrence of the first primary efficacy endpoint event in the two treatment groups.

Figure 8: Time to First Occurrence of the Composite of Recurrent DVT or Non-fatal or Fatal PE by Treatment Group (Full Analysis Set) – EINSTEIN CHOICE Study

14.4 Prophylaxis of Deep Vein Thrombosis Following Hip or Knee Replacement Surgery

XARELTO was studied in 9011 patients (4487 XARELTO-treated, 4524 enoxaparin-treated patients) in the REgulation of Coagulation in ORthopedic Surgery to Prevent DVT and PE, Controlled, Double-blind, Randomized Study of BAY 59-7939 in the Extended Prevention of VTE in Patients Undergoing Elective Total Hip or Knee Replacement (RECORD 1, 2, and 3) [NCT00329628, NCT00332020, NCT00361894] studies.

The two randomized, double-blind, clinical studies (RECORD 1 and 2) in patients undergoing elective total hip replacement surgery compared XARELTO 10 mg once daily starting at least 6 to 8 hours (about 90% of patients dosed 6 to 10 hours) after wound closure versus enoxaparin 40 mg once daily started 12 hours preoperatively. In RECORD 1 and 2, a total of 6727 patients were randomized and 6579 received study drug. The mean age [± standard deviation (SD)] was 63 ± 12.2 (range 18 to 93) years with 49% of patients ≥65 years and 55% of patients were female. More than 82% of patients were White, 7% were Asian, and less than 2% were Black. The studies excluded patients undergoing staged bilateral total hip replacement, patients with severe renal impairment defined as an estimated creatinine clearance <30 mL/min, or patients with significant liver disease (hepatitis or cirrhosis). In RECORD 1, the mean exposure duration (± SD) to active XARELTO and enoxaparin was 33.3 ± 7.0 and 33.6 ± 8.3 days, respectively. In RECORD 2, the mean exposure duration to active XARELTO and enoxaparin was 33.5 ± 6.9 and 12.4 ± 2.9 days, respectively. After Day 13, oral placebo was continued in the enoxaparin group for the remainder of the double-blind study duration. The efficacy data for RECORD 1 and 2 are provided in Table 22.

Table 22: Summary of Key Efficacy Analysis Results for Patients Undergoing Total Hip Replacement Surgery - Modified Intent-to-Treat Population
 | RECORD 1 |  |  | RECORD 2
Treatment Dosage and Duration | XARELTO 10 mg once daily | Enoxaparin 40 mg once daily | RRR [Relative Risk Reduction; CI = confidence interval] , p-value | XARELTO 10 mg once daily | Enoxaparin [Includes the placebo-controlled period of RECORD 2] 40 mg once daily | RRR , p-value
Number of Patients | N=1513 | N=1473 |  | N=834 | N=835
Total VTE | 17 (1.1%) | 57 (3.9%) | 71% (95% CI: 50, 83), p<0.001 | 17 (2.0%) | 70 (8.4%) | 76% (95% CI: 59, 86), p<0.001
Components of Total VTE
Proximal DVT | 1 (0.1%) | 31 (2.1%) |  | 5 (0.6%) | 40 (4.8%)
Distal DVT | 12 (0.8%) | 26 (1.8%) |  | 11 (1.3%) | 43 (5.2%)
Non-fatal PE | 3 (0.2%) | 1 (0.1%) |  | 1 (0.1%) | 4 (0.5%)
Death (any cause) | 4 (0.3%) | 4 (0.3%) |  | 2 (0.2%) | 4 (0.5%)
Number of Patients | N=1600 | N=1587 |  | N=928 | N=929
Major VTE [Proximal DVT, nonfatal PE or VTE-related death] | 3 (0.2%) | 33 (2.1%) | 91% (95% CI: 71, 97), p<0.001 | 6 (0.7%) | 45 (4.8%) | 87% (95% CI: 69, 94), p<0.001
Number of Patients | N=2103 | N=2119 |  | N=1178 | N=1179
Symptomatic VTE | 5 (0.2%) | 11 (0.5%) |  | 3 (0.3%) | 15 (1.3%)

One randomized, double-blind, clinical study (RECORD 3) in patients undergoing elective total knee replacement surgery compared XARELTO 10 mg once daily started at least 6 to 8 hours (about 90% of patients dosed 6 to 10 hours) after wound closure versus enoxaparin. In RECORD 3, the enoxaparin regimen was 40 mg once daily started 12 hours preoperatively. The mean age (± SD) of patients in the study was 68 ± 9.0 (range 28 to 91) years with 66% of patients ≥65 years. Sixty-eight percent (68%) of patients were female. Eighty-one percent (81%) of patients were White, less than 7% were Asian, and less than 2% were Black. The study excluded patients with severe renal impairment defined as an estimated creatinine clearance <30 mL/min or patients with significant liver disease (hepatitis or cirrhosis). The mean exposure duration (± SD) to active XARELTO and enoxaparin was 11.9 ± 2.3 and 12.5 ± 3.0 days, respectively. The efficacy data are provided in Table 23.

Table 23: Summary of Key Efficacy Analysis Results for Patients Undergoing Total Knee Replacement Surgery - Modified Intent-to-Treat Population
 | RECORD 3
Treatment Dosage and Duration | XARELTO 10 mg once daily | Enoxaparin 40 mg once daily | RRR [Relative Risk Reduction; CI = confidence interval] , p-value
Number of Patients | N=813 | N=871
Total VTE | 79 (9.7%) | 164 (18.8%) | 48% (95% CI: 34, 60), p<0.001
Components of events contributing to Total VTE
Proximal DVT | 9 (1.1%) | 19 (2.2%)
Distal DVT | 74 (9.1%) | 154 (17.7%)
Non-fatal PE | 0 | 4 (0.5%)
Death (any cause) | 0 | 2 (0.2%)
Number of Patients | N=895 | N=917
Major VTE [Proximal DVT, nonfatal PE or VTE-related death] | 9 (1.0%) | 23 (2.5%) | 60% (95% CI: 14, 81), p = 0.024
Number of Patients | N=1206 | N=1226
Symptomatic VTE | 8 (0.7%) | 24 (2.0%)

14.5 Prophylaxis of Venous Thromboembolism in Acutely Ill Medical Patients at Risk for Thromboembolic Complications Not at High Risk of Bleeding

The efficacy and safety of XARELTO for prophylaxis of venous thromboembolism in acutely ill medical patients at risk for thromboembolic complications not at high risk of bleeding was evaluated in the MAGELLAN study (Multicenter, r Andomized, parallel Group Efficacy and safety study for the prevention of venous thromboembolism in hospitalized medically i LLpatients comparing rivaroxab aNwith enoxaparin [NCT00571649]). MAGELLAN was a multicenter, randomized, double-blind, parallel-group efficacy and safety study comparing XARELTO to enoxaparin, in the prevention of VTE in hospitalized acutely ill medical patients during the in-hospital and post-hospital discharge period. Eligible patients included adults who were at least 40 years of age, hospitalized for an acute medical illness, at risk of VTE due to moderate or severe immobility, and had additional risk factors for VTE. The population at risk of VTE was required to have one or more of the following VTE risk factors, i.e. prolonged immobilization, age ≥75 years, history of cancer, history of VTE, history of heart failure, thrombophilia, acute infectious disease contributing to the hospitalization and BMI ≥35 kg/m^2). The causes for hospitalization included heart failure, active cancer, acute ischemic stroke, acute infectious and inflammatory disease and acute respiratory insufficiency. Patients were randomized to receive either XARELTO 10 mg once daily for 35 ±4 days starting in hospital and continuing post hospital discharge (n=4050) or enoxaparin 40 mg once daily for 10 ±4 days starting in hospital followed by placebo post-discharge (n=4051).

The major efficacy outcome in the MAGELLAN trial was a composite endpoint that included asymptomatic proximal deep venous thrombosis (DVT) in lower extremity, symptomatic proximal or distal DVT in the lower extremity, symptomatic non-fatal pulmonary embolism (PE), and death related to venous thromboembolism (VTE).

A total of 6024 patients were evaluable for the major efficacy outcome analysis (2967 on XARELTO 10 mg once daily and 3057 on enoxaparin/placebo). The mean age was 68.9 years, with 37.1% of the subject population ≥ 75 years. VTE risk factors included severe immobilization at study entry (99.9%), D-dimer > 2× ULN (43.7%), history of heart failure (35.6%), BMI ≥ 35 kg/m ^2(15.2%), chronic venous insufficiency (14.9%), acute infectious disease (13.9%), severe varicosis (12.5%), history of cancer (16.2%), history of VTE (4.5%), hormone replacement therapy (1.1%), and thrombophilia (0.3%), recent major surgery (0.8%) and recent serious trauma (0.2%). The population was 54.7% male, 68.2% White, 20.4% Asian, 1.9% Black and 5.3% Other. Admitting diagnoses for hospitalization were acute infectious diseases (43.8%) followed by congestive heart failure NYHA class III or IV (33.2%), acute respiratory insufficiency (26.4%), acute ischemic stroke (18.5%) and acute inflammatory diseases (3.4%).

Table 24 shows the overall results from the prespecified, modified intent-to-treat (mITT) analysis for the efficacy outcomes and their components. This analysis excludes approximately 25% of the patients mainly due to no ultrasonographic assessment (13.5%), inadequate assessment at day 35 (8.1%), or lack of intake of study medication (1.3%).

Table 24: Efficacy Results at Day 35 (modified Intent-to-Treat) and at Day 10 (per protocol) in the MAGELLAN Study
Events from Day 1 to Day 35, mITT analysis set | XARELTO 10 mg N=2967 n (%) | Enoxaparin 40 mg/placebo N=3057 n (%) | RR (95% CI)
Primary Composite Endpoint at Day 35 | 131 (4.4%) | 175 (5.7%) | 0.77 (0.62, 0.96)
Symptomatic non-fatal PE | 10 (0.3) | 14 (0.5)
Symptomatic DVT in lower extremity | 13 (0.4) | 15 (0.5)
Asymptomatic proximal DVT in lower extremity | 103 (3.5) | 133 (4.4)
VTE related death | 19 (0.6) | 30 (1.0)
Events from Day 1 to Day 10, PP analysis set | XARELTO 10 mg N=2938 n (%) | Enoxaparin 40 mg N=2993 n (%) | RR (95% CI)
Primary Composite Endpoint at Day 10 | 78 (2.7) | 82 (2.7) | 0.97 (0.71, 1.31)
Symptomatic non-fatal PE | 6 (0.2) | 2 (<0.1)
Symptomatic DVT in lower extremity | 7 (0.2) | 6 (0.2)
Asymptomatic proximal DVT in lower extremity | 71 (2.4) | 71 (2.4)
VTE related death | 3 (0.1) | 6 (0.2)
mITT analysis set plus all-cause mortality | N=3096 n (%) | N=3169 n (%) | RR (95% CI)
Other Composite Endpoint at Day 35 | 266 (8.6) | 293 (9.2) | 0.93 (0.80, 1.09)
Symptomatic non-fatal PE | 10 (0.3) | 14 (0.4)
Symptomatic DVT in lower extremity | 13 (0.4) | 15 (0.5)
Asymptomatic proximal DVT in lower extremity | 103 (3.3) | 133 (4.2)
All-cause mortality | 159 (5.1) | 153 (4.8)
mITT: modified intent-to-treat; PP: per protocol; DVT: Deep vein thrombosis; PE: pulmonary embolism; VTE: venous thromboembolism; CI: Confidence Interval; RR: Relative Risk

Patients with bronchiectasis/pulmonary cavitation, active cancer, dual antiplatelet therapy or active gastroduodenal ulcer or any bleeding in the previous three months (19.4%) all had an excess of bleeding with XARELTO compared with enoxaparin/placebo. Therefore, patients meeting these criteria were excluded from the following analyses presented below.

Table 25 provides the efficacy results for the subgroup of patients not at a high risk of bleeding.

Table 25: Efficacy Results at Day 35 (modified Intent-to-Treat) and at Day 10 (per protocol) in patients not at a high risk of bleeding in the MAGELLAN Study [Patients at high risk of bleeding (i.e. bronchiectasis/pulmonary cavitation, active cancer, dual antiplatelet therapy or active gastroduodenal ulcer or any bleeding in the previous three months) were excluded.]
Events from Day 1 to Day 35, mITT analysis set | XARELTO 10 mg N=2419 n (%) | Enoxaparin 40 mg/placebo N=2506 n (%) | RR (95% CI)
Primary Composite Endpoint at Day 35 | 94 (3.9) | 143 (5.7) | 0.68 (0.53, 0.88)
Symptomatic non-fatal PE | 7 (0.3) | 10 (0.4)
Symptomatic DVT in lower extremity | 9 (0.4) | 10 (0.4)
Asymptomatic proximal DVT in lower extremity | 73 (3.0) | 110 (4.4)
VTE related death | 15 (0.6) | 26 (1.0)
Events from Day 1 to Day 10, PP analysis set | XARELTO 10 mg N=2385 n (%) | Enoxaparin 40 mg N=2433 n (%) | RR (95% CI)
Primary Composite Endpoint at Day 10 | 58 (2.4) | 72 (3.0) | 0.82 (0.58, 1.15)
Symptomatic non-fatal PE | 5 (0.2) | 2 (<0.1)
Symptomatic DVT in lower extremity | 6 (0.3) | 4 (0.2)
Asymptomatic proximal DVT in lower extremity | 52 (2.2) | 62 (2.5)
VTE related death | 2 (<0.1) | 6 (0.2)
mITT analysis set plus all-cause mortality | N=2504 n (%) | N=2583 n (%) | RR (95% CI)
Other Composite Endpoint at Day 35 | 184 (7.3) | 225 (8.7) | 0.84 (0.70, 1.02)
Symptomatic non-fatal PE | 7 (0.3) | 10 (0.4)
Symptomatic DVT in lower extremity | 9 (0.4) | 10 (0.4)
Asymptomatic proximal DVT in lower extremity | 73 (2.9) | 110 (4.3)
All-cause mortality | 107 (4.3) | 112 (4.3)
mITT: modified intent-to-treat; PP: per protocol; DVT: Deep vein thrombosis; PE: pulmonary embolism; VTE: venous thromboembolism; CI: Confidence Interval; RR: Relative Risk

14.6 Reduction of Risk of Major Cardiovascular Events in Patients with CAD

The evidence for the efficacy and safety of XARELTO for the reduction in the risk of stroke, myocardial infarction, or cardiovascular death in patients with coronary artery disease (CAD) or peripheral artery disease (PAD) was derived from the double-blind, placebo-controlled Cardiovascular Outco Mes for People using Anticoagulation Strategie Strial (COMPASS) [NCT10776424]. A total of 27,395 patients were evenly randomized to rivaroxaban 2.5 mg orally twice daily plus aspirin 100 mg once daily, rivaroxaban 5 mg orally twice daily alone, or aspirin 100 mg once daily alone. Because the 5 mg dose alone was not superior to aspirin alone, only the data concerning the 2.5 mg dose plus aspirin are discussed below.

Patients with established CAD or PAD were eligible. Patients with CAD who were younger than 65 years of age were also required to have documentation of atherosclerosis involving at least two vascular beds or to have at least two additional cardiovascular risk factors (current smoking, diabetes mellitus, an estimated glomerular filtration rate [eGFR] <60 mL per minute, heart failure, or non-lacunar ischemic stroke ≥1 month earlier). Patients with PAD were either symptomatic with ankle brachial index <0.90 or had asymptomatic carotid artery stenosis ≥50%, a previous carotid revascularization procedure, or established ischemic disease of one or both lower extremities. Patients were excluded for use of dual antiplatelet, other non-aspirin antiplatelet, or oral anticoagulant therapies, ischemic, non-lacunar stroke within 1 month, hemorrhagic or lacunar stroke at any time, or eGFR <15 mL/min.

The mean age was 68 years and 21% of the subject population were ≥75 years. Of the included patients, 91% had CAD (and will be referred to as the COMPASS CAD population), 27% had PAD (and will be referred to as the COMPASS PAD population), and 18% had both CAD and PAD. Of the patients with CAD, 69% had prior MI, 60% had prior percutaneous transluminal coronary angioplasty (PTCA)/atherectomy/ percutaneous coronary intervention (PCI), and 26% had history of coronary artery bypass grafting (CABG) prior to study. Of the patients with PAD, 49% had intermittent claudication, 27% had peripheral artery bypass surgery or peripheral percutaneous transluminal angioplasty, 26% had asymptomatic carotid artery stenosis > 50%, and 4% had limb or foot amputation for arterial vascular disease.

The mean duration of follow-up was 23 months. Relative to placebo, XARELTO reduced the rate of the primary composite outcome of stroke, myocardial infarction or cardiovascular death: HR 0.76 (95% CI: 0.66, 0.86; p=0.00004). In the COMPASS CAD population, the benefit was observed early with a constant treatment effect over the entire treatment period (see Table 26 and Figure 10).

A benefit-risk analysis of the data from COMPASS was performed by comparing the number of CV events (CV deaths, myocardial infarctions and non-hemorrhagic strokes) prevented to the number of fatal or life-threatening bleeding events (fatal bleeds + symptomatic non-fatal bleeds into a critical organ) in the XARELTO group versus the placebo group. Compared to placebo, during 10,000 patient-years of treatment, XARELTO would be expected to result in 70 fewer CV events and 12 additional life-threatening bleeds, indicating a favorable balance of benefits and risks.

The results in the COMPASS CAD population were consistent across major subgroups (see Figure 9).

Figure 9: Risk of Primary Efficacy Outcome by Baseline Characteristics in the COMPASS CAD Population (Intent-to-Treat Population) [All patients received aspirin 100 mg once daily as background therapy.]

Table 26: Efficacy results from COMPASS CAD Population [intention to treat analysis set, primary analyses.]
Event | XARELTO [Treatment schedule: XARELTO 2.5 mg twice daily vs placebo. All patients received aspirin 100 mg once daily as background therapy.] N=8313 |  | Placebo N=8261 |  | Hazard Ratio (95% CI) [XARELTO vs. placebo.]
Event | n (%) | Event Rate (%/year) | n (%) | Event Rate (%/year) | Hazard Ratio (95% CI) [XARELTO vs. placebo.]
Stroke, MI or CV death | 347 (4.2) | 2.2 | 460 (5.6) | 2.9 | 0.74 (0.65, 0.86)
- Stroke | 74 (0.9) | 0.5 | 130 (1.6) | 0.8 | 0.56 (0.42, 0.75)
- MI | 169 (2.0) | 1.1 | 195 (2.4) | 1.2 | 0.86 (0.70, 1.05)
- CV death | 139 (1.7) | 0.9 | 184 (2.2) | 1.1 | 0.75 (0.60, 0.93)
Coronary heart disease death, MI, ischemic stroke, acute limb ischemia | 299 (3.6) | 1.9 | 411 (5.0) | 2.6 | 0.72 (0.62, 0.83)
- Coronary heart disease death [Coronary heart disease death: death due to acute MI, sudden cardiac death, or CV procedure.] | 80 (1.0) | 0.5 | 107 (1.3) | 0.7 | 0.74 (0.55, 0.99)
- Ischemic stroke | 56 (0.7) | 0.3 | 114 (1.4) | 0.7 | 0.49 (0.35, 0.67)
- Acute limb ischemia [Acute limb ischemia is defined as limb-threatening ischemia leading to an acute vascular intervention (i.e., pharmacologic, peripheral arterial surgery/reconstruction, peripheral angioplasty/stent, or amputation).] | 13 (0.2) | 0.1 | 27 (0.3) | 0.2 | 0.48 (0.25, 0.93)
CV death, [CV death includes CHD death, or death due to other CV causes or unknown death.] MI, ischemic stroke, acute limb ischemia | 349 (4.2) | 2.2 | 470 (5.7) | 3.0 | 0.73 (0.64, 0.84)
All-cause mortality | 262 (3.2) | 1.6 | 339 (4.1) | 2.1 | 0.77 (0.65, 0.90)
CHD: coronary heart disease, CI: confidence interval; CV: cardiovascular; MI: myocardial infarction

Figure 10: Time to First Occurrence of Primary Efficacy Outcome (Stroke, Myocardial Infarction, Cardiovascular Death) in the COMPASS CAD Population [All patients received aspirin 100 mg once daily as background therapy.]

CI: confidence interval

14.7 Reduction of Risk of Major Thrombotic Vascular Events in Patients with PAD, Including Patients after Lower Extremity Revascularization due to Symptomatic PAD

The efficacy and safety of XARELTO 2.5 mg orally twice daily versus placebo on a background of aspirin 100 mg once daily in patients with PAD were evaluated in the COMPASS study (n=4996) and will be referred to as the COMPASS PAD population [see Clinical Studies (14.6)].

The efficacy and safety of XARELTO were also evaluated for the reduction in the risk of the composite endpoint of myocardial infarction, ischemic stroke, cardiovascular death, acute limb ischemia (ALI), and major amputation of a vascular etiology in patients undergoing a lower extremity infrainguinal revascularization procedure due to symptomatic peripheral artery disease (PAD) in the double-blinded, placebo-controlled Vascular Outcomes stud Yof ASA alon Gwith rivaroxaban in Endovascular or surgical limb Revascularization for peripheral artery disease (PAD) trial (VOYAGER) [NCT02504216]. A total of 6,564 patients were equally randomized to XARELTO 2.5 mg orally twice daily vs placebo on a background therapy of aspirin 100 mg once daily.

Eligible patients included adults who were at least 50 years of age with documented moderate to severe symptomatic lower extremity atherosclerotic PAD who had a successful peripheral surgical procedure and/or endovascular procedure with or without clopidogrel (up to a maximum of 6 months was allowed; median duration of therapy was 31 days). Patients had either a prior history of limb revascularization with ankle brachial index ≤0.85 or no prior history of limb revascularization with ankle brachial index ≤0.80. Patients in need of dual antiplatelet for >6 months, or any additional antiplatelet other than aspirin and clopidogrel, or oral anticoagulant, as well as patients with a history of intracranial hemorrhage, stroke, or transient ischemic attack (TIA), or patients with eGFR <15 mL/min were excluded.

The mean age was 67 years and 20% of the subject population was ≥75 years. Of the included patients, 35% had surgical revascularization, 47% had endovascular revascularization with clopidogrel, and 18% endovascular revascularization without clopidogrel. The median duration of follow-up was 30.8 months.

XARELTO 2.5 mg twice daily was superior to placebo in reducing the rate of the primary composite outcome of myocardial infarction, ischemic stroke, cardiovascular death, acute limb ischemia (ALI), and major amputation of a vascular etiology. The primary efficacy outcome and its components are provided in Table 27. The Kaplan-Meier plot for the primary efficacy outcome can be seen in Figure 11. The secondary efficacy outcomes were tested for superiority in a prespecified, hierarchical order and the first five of seven endpoints were significantly reduced in the rivaroxaban treatment arm (see Table 27). Compared to placebo during 10,000 patient-years of treatment, XARELTO would be expected to result in 181 fewer primary outcome events and 29 more TIMI major bleeding events, indicating a favorable balance of benefits and risks.

Figure 11: Time to First Occurrence of Primary Efficacy Outcome (Myocardial Infarction, Ischemic Stroke, Cardiovascular Death, Acute Limb Ischemia, Major Amputation due to Vascular Origins) in VOYAGER [All patients received aspirin 100 mg once daily as background therapy.]

Figure 12 shows the risk of primary efficacy outcome across major subgroups. Subgroup analyses must be interpreted cautiously, as differences can reflect the play of chance among a large number of analyses. The primary efficacy endpoint generally shows homogeneous results across subgroups.

Figure 12: Risk of Primary Efficacy Outcome by Baseline Characteristics in VOYAGER (Intent-to-Treat Population) [All patients received aspirin 100 mg once daily as background therapy.]

Table 27 provides the efficacy event rates for the prespecified endpoints in VOYAGER and similar endpoints in the COMPASS PAD population.

Table 27: Efficacy Results in VOYAGER (Intent-to-Treat Population) and COMPASS PAD
 | VOYAGER |  |  | COMPASS PAD
 | XARELTO N=3286 | Placebo N=3278 | Hazard Ratio (95% CI) [XARELTO vs. placebo.] p-value [Two-sided p-values] | XARELTO N=2492 | Placebo N=2504 | Hazard Ratio (95% CI)
Outcome Components | Event Rate (%/year) |  | Hazard Ratio (95% CI) [XARELTO vs. placebo.] p-value [Two-sided p-values] | Event Rate (%/year) |  | Hazard Ratio (95% CI)
5-Component Outcome (Major thrombotic vascular events) [Major thrombotic vascular event is the composite of MI, ischemic stroke, CV death, ALI, and major amputation of a vascular etiology.] | 6.8 | 8.0 | 0.85 (0.76, 0.96) p=0.0085 | 3.4 | 4.8 | 0.71 (0.57, 0.87)
MI | 1.7 | 1.9 | 0.88 (0.70, 1.12) | 1.1 | 1.5 | 0.76 (0.53, 1.09)
Ischemic Stroke [Ischemic stroke for VOYAGER included stroke of uncertain/unknown etiology whereas COMPASS only included ischemic stroke.] | 0.9 | 1.0 | 0.87 (0.63, 1.19) | 0.5 | 0.9 | 0.55 (0.33, 0.93)
CV death [CV death includes Coronary Heart Disease death, or death due to other CV causes or sudden cardiac arrest and unknown death.] | 2.5 | 2.2 | 1.14 (0.93, 1.40) | 1.4 | 1.7 | 0.82 (0.59, 1.14)
ALI | 2.0 | 3.0 | 0.67 (0.55, 0.82) | 0.4 | 0.8 | 0.56 (0.32, 0.99)
Major amputation of a vascular etiology [Adjudicated events in VOYAGER and investigator reported events in COMPASS] | 1.3 | 1.5 | 0.89 (0.68, 1.16) | 0.2 | 0.6 | 0.40 (0.20, 0.79)
VOYAGER Secondary Efficacy Outcomes [Secondary outcomes for VOYAGER were tested sequentially.]
MI, ischemic stroke, CHD death, [CHD death includes death due to sudden cardiac death, MI, or coronary revascularization procedure] ALI, and major amputation due to vascular etiology | 5.8 | 7.3 | 0.80 (0.71, 0.91) p=0.0008 | 2.8 | 4.2 | 0.66 (0.53, 0.83)
Unplanned index limb revascularization for recurrent limb ischemia [Unplanned index limb revascularization for recurrent limb ischemia was not captured in COMPASS study.] | 8.4 | 9.5 | 0.88 (0.79, 0.99) p=0.028 | N/A | N/A | N/A
Hospitalization for a coronary or peripheral cause of a thrombotic nature | 3.5 | 4.8 | 0.72 (0.62, 0.85) p<0.0001 | 1.7 | 2.9 | 0.58 (0.44, 0.77)
MI, ischemic stroke, all-cause mortality, ALI, and major amputation due to vascular etiology | 8.2 | 9.3 | 0.89 (0.79, 0.99) p=0.029 | 4.8 | 6.0 | 0.80 (0.67, 0.96)
MI, all-cause stroke, CV death, ALI, and major amputation due to vascular etiology | 6.9 | 8.1 | 0.86 (0.76, 0.96) p=0.010 | 3.4 | 4.9 | 0.70 (0.57, 0.86)
All-cause mortality | 4.0 | 3.7 | 1.08 (0.92, 1.27) | 2.8 | 3.1 | 0.91 (0.72, 1.16)
VTE events [Investigator reported in VOYAGER and adjudicated events in COMPASS] | 0.3 | 0.5 | 0.61 (0.37, 1.00) | 0.2 | 0.3 | 0.67 (0.30, 1.49)
Efficacy endpoints in COMPASS PAD were analysed according to the pre-specified endpoints in VOYAGER when applicable.
ALI=acute limb ischemia, CHD=coronary heart disease; CI=confidence interval, CV=cardiovascular; MI=myocardial infarction, VTE=venous thromboembolism.

14.8 Treatment of Venous Thromboembolism and Reduction in Risk of Recurrent Venous Thromboembolism in Pediatric Patients

XARELTO for the treatment of venous thromboembolism (VTE) and reduction in the risk of recurrent VTE was evaluated in the EINSTEIN Junior Phase 3 study [NCT02234843], a multicenter, open-label, active-controlled, randomized study in 500 pediatric patients from birth to less than 18 years with confirmed VTE. There were 276 children aged 12 to <18 years, 101 children aged 6 to <12 years, 69 children aged 2 to <6 years, and 54 children aged <2 years. Patients <6 months of age were excluded from enrollment if they were <37 weeks of gestation at birth, or had <10 days of oral feeding, or had a body weight of <2.6 kg.

Index VTE was classified as either central venous catheter-related VTE (CVC-VTE), cerebral vein and sinus thrombosis (CVST), and all other VTE including DVT and PE (non-CVC-VTE).

Patients received initial treatment with therapeutic dosages of unfractionated heparin (UFH), low molecular weight heparin (LMWH), or fondaparinux for at least 5 days, and were randomized 2:1 to receive either body weight-adjusted doses of XARELTO (exposures to match that of 20 mg daily dose in adults) or comparator group (UFH, LMWH, fondaparinux or VKA) for a main study treatment period of 3 months (or 1 month for children <2 years with CVC-VTE). A diagnostic imaging test was obtained at baseline and at the end of the main study treatment. When clinically necessary, treatment was extended up to 12 months in total (or up to 3 months in total for children <2 years with CVC-VTE).

Table 28 displays the primary and secondary efficacy results.

Table 28: Efficacy Results in EINSTEIN Junior Study – Full Analysis Set
Event | XARELTO [Treatment schedule: body weight-adjusted doses of XARELTO (exposures to match that of 20 mg daily dose in adults); randomized 2:1 (XARELTO: Comparator).] N=335 n (%) (95% CI) [Confidence intervals for incidence proportion were calculated by applying the method of Blyth-Still-Casella.] | Comparator Group [Unfractionated heparin (UFH), low molecular weight heparin (LMWH), fondaparinux or VKA.] N=165 n (%) (95% CI) | XARELTO vs. Comparator Group Risk Difference (95% CI) [Confidence intervals for difference in incidence proportions were calculated by unstratified exact method according to Agresti-Min using the standardized test statistic and inverting a two-sided test.] | XARELTO vs. Comparator Group Hazard Ratio (95% CI)
Primary efficacy outcome: Symptomatic recurrent VTE | 4 (1.2) (0.4%, 3.0%) | 5 (3.0) (1.2%, 6.6%) | -1.8% (-6.0%, 0.6%) | 0.40 (0.11, 1.41)
Secondary efficacy outcome: Symptomatic recurrent VTE or asymptomatic deterioration on repeat imaging | 5 (1.5) (0.6%, 3.4%) | 6 (3.6) (1.6%, 7.6%) | -2.1% (-6.5%, 0.6%)

Complete resolution of thrombus on repeat imaging without recurrent VTE occurred in 128 of 335 children (38.2%, 95% CI 33.0%, 43.5%) in the XARELTO group and 43 of 165 children (26.1%, 95% CI 19.8%, 33.0%) in the comparator group. Symptomatic recurrent VTE or major bleeding events occurred in 4 of 335 children (1.2%, 95% CI 0.4%, 3.0%) in the XARELTO group and 7 of 165 children (4.2%, 95% CI 2.0%, 8.4%) in the comparator group.

14.9 Thromboprophylaxis in Pediatric Patients with Congenital Heart Disease after the Fontan Procedure

The efficacy and safety of XARELTO for thromboprophylaxis in pediatric patients with congenital heart disease who have undergone the Fontan procedure was evaluated in the UNIVERSE Phase 3 study [NCT02846532]. UNIVERSE was a prospective, open-label, active controlled, multicenter, 2-part study, designed to evaluate the single- and multiple-dose pharmacokinetic properties of XARELTO (Part A), and to evaluate the safety and efficacy of XARELTO when used for thromboprophylaxis for 12 months compared with aspirin (Part B) in children 2 to 8 years of age with single ventricle physiology who had the Fontan procedure. Patients in Part B were randomized 2:1 to receive either body weight-adjusted doses of XARELTO (exposures to match that of 10 mg daily dose in adults) or aspirin (approximately 5 mg/kg). Patients with eGFR <30 ml/min/1.73 m^2were excluded.

The median time between Fontan procedure and the first dose of XARELTO was 4 (range: 2–61) days in Part A and 34 (range: 2–124) days in part B. In comparison, the median time to initiating aspirin was 24 (range 2–117) days.

Table 29 displays the primary efficacy results.

Table 29: Efficacy Results in UNIVERSE Study – Full Analysis Set
 | Part A [Part A: single arm; not randomized] | Part B [Part B: randomized 2:1 (XARELTO: Aspirin)]
Event | XARELTO N=12 n (%) (95% CI) [Confidence intervals for incidence proportion were calculated by applying the method of Blyth-Still-Casella.] | XARELTO [Treatment schedule: body weight-adjusted doses of XARELTO (exposures to match that of 10 mg daily dose in adults) or aspirin (approximately 5 mg/kg)] N=64 n (%) (95% CI) | Aspirin N=34 n (%) (95% CI) | XARELTO vs. Aspirin Risk Difference (95% CI) [Confidence intervals for difference in incidence proportions were calculated by unstratified exact method according to Agresti-Min using the standardized test statistic and inverting a two-sided test.]
Primary efficacy outcome: any thrombotic event | 1 (8.3) (0.4%, 34.9%) | 1 (1.6) (0.1%, 7.8%) | 3 (8.8) (2.4%, 22.2%) | -7.3% (-21.7%, 1.1%)
Ischemic stroke | 0 (0.0%, 23.6%) | 0 (0.0%, 5.6%) | 1 (2.9) 0.2%, 15.1%) | -2.9% (-16.2%, 2.9%)
Pulmonary embolism | 0 (0.0%, 23.6%) | 1 (1.6) (0.1%, 7.8%) | 0 (0.0%, 9.0%) | 1.6% (-9.9%, 8.4%)
Venous thrombosis | 1 (8.3) (0.4%, 34.9%) | 0 (0.0%, 5.6%) | 2 (5.9) (1.1%, 18.8%) | -5.9% (-20.6%, -0.1%)

16 HOW SUPPLIED/STORAGE AND HANDLING

XARELTO ®(rivaroxaban) Tablets are available in the strengths and packages listed below:

- 10 mg tablets are round, light red, biconvex film-coated tablets marked with a triangle pointing down above a "10" on one side, and "Xa" on the other side. The tablets are supplied in the packages listed:

Overbagged with 10 film-coated tablets per bag, NDC 55154-1422-0 WARNING: This Unit Dose package is not child resistant and is Intended for Institutional Use Only. Keep this and all drugs out of the reach of children.

- 15 mg tablets are round, red, biconvex film-coated tablets with a triangle pointing down above a "15" marked on one side and "Xa" on the other side. The tablets are supplied in the packages listed:

Bottles of approximately 2070 film-coated tablets, NDC 55154-1424-8

- 20 mg tablets are triangle-shaped, dark red film-coated tablets with a triangle pointing down above a "20" marked on one side and "Xa" on the other side. The tablets are supplied in the packages listed:

Bottles of approximately 4440 film-coated tablets, NDC 55154-1423-8

Storage of tablets, granules and reconstituted suspension:

Store at room temperature between 20 °C to 25 °C (68 °F to 77 °F); excursions permitted between 15 °C to 30 °C (59 °F to 86 °F) [see USP Controlled Room Temperature].

Do not freeze the granules or reconstituted suspension.

Keep out of the reach of children.

17 PATIENT COUNSELING INFORMATION

For the tablets, advise the patient and/or caregiver to read the FDA-approved patient labeling (Medication Guide).

For the suspension, advise the patient and/or caregiver to read the FDA-approved patient labeling (Medication Guide and Instructions for Use).

Instructions for Patient Use

- Advise patients to take XARELTO only as directed.
- Remind patients to not discontinue XARELTO without first talking to their healthcare professional.

Adults

- Advise patients with atrial fibrillation to take XARELTO once daily with the evening meal.
- Advise patients for initial treatment of DVT and/or PE to take XARELTO 15 mg or 20 mg tablets with food at approximately the same time every day [see Dosage and Administration (2.1)].
- Advise patients who are at a continued risk of recurrent DVT and/or PE after at least 6 months of initial treatment, to take XARELTO 10 mg once daily with or without food [see Dosage and Administration (2.1)].
- Advise patients who cannot swallow the tablet whole to crush XARELTO and combine with a small amount of applesauce followed by food [see Dosage and Administration (2.6)].
- For patients requiring an NG tube or gastric feeding tube, instruct the patient or caregiver to crush the XARELTO tablet and mix it with a small amount of water before administering via the tube [see Dosage and Administration (2.6)].
- If a dose is missed, advise the patient according to the instructions in the Full Prescribing Information based on their dosing schedule [see Dosage and Administration (2.5)].

Pediatric Patients

- The adult caregiver should administer the dose. Advise caregivers to use the syringes provided in the original carton.
- Advise the caregiver whether the dose needs to be taken with food or not [see Dosage and Administration (2.2)].
- Advise the caregiver the tablet must not be split in an attempt to provide a fraction of a tablet dose [see Dosage and Administration (2.2)].
- If a child vomits or spits up the dose within 30 minutes after receiving the dose, a new dose should be given. However, if the child vomits more than 30 minutes after the dose is taken, the dose should not be re-administered and the next dose should be taken as scheduled. If a child vomits or spits up the dose repeatedly, the caregiver should contact the child's doctor right away [see Dosage and Administration (2.2)].
- For children who are unable to swallow whole tablets, XARELTO oral suspension may be used.
- If a dose is missed, advise the patient according to the instructions in the Full Prescribing Information based on their dosing schedule [see Dosage and Administration (2.5)].

Bleeding Risks

- Advise patients to report any unusual bleeding or bruising to their physician. Inform patients that it might take them longer than usual to stop bleeding, and that they may bruise and/or bleed more easily when they are treated with XARELTO [see Warnings and Precautions (5.2)].
- If patients have had neuraxial anesthesia or spinal puncture, and particularly, if they are taking concomitant NSAIDs or platelet inhibitors, advise patients to watch for signs and symptoms of spinal or epidural hematoma, such as back pain, tingling, numbness (especially in the lower limbs), muscle weakness, and stool or urine incontinence. If any of these symptoms occur, advise the patient to contact his or her physician immediately [see Boxed Warning].

Invasive or Surgical Procedures

Instruct patients to inform their healthcare professional that they are taking XARELTO before any invasive procedure (including dental procedures) is scheduled.

Concomitant Medication and Herbals

Advise patients to inform their physicians and dentists if they are taking, or plan to take, any prescription or over-the-counter drugs or herbals, so their healthcare professionals can evaluate potential interactions [see Drug Interactions (7)].

Pregnancy and Pregnancy-Related Hemorrhage

- Advise patients to inform their physician immediately if they become pregnant or intend to become pregnant during treatment with XARELTO [see Use in Specific Populations (8.1)].
- Advise pregnant women receiving XARELTO to immediately report to their physician any bleeding or symptoms of blood loss [see Warnings and Precautions (5.7)].

Lactation

Advise patients to discuss with their physician the benefits and risks of XARELTO for the mother and for the child if they are nursing or intend to nurse during anticoagulant treatment [see Use in Specific Populations (8.2)].

Females and Males of Reproductive Potential

Advise patients who can become pregnant to discuss pregnancy planning with their physician [see Use in Specific Populations (8.3)].

Manufactured for:
Janssen Pharmaceuticals, Inc.
Titusville, NJ 08560, USA

Licensed from:
Bayer HealthCare AG
51368 Leverkusen, Germany

For patent information: www.janssenpatents.com

© Johnson & Johnson and its affiliates 2011-2021, 2025

Distributed By:

Cardinal Health

Dublin, OH 43017

L49750740324

ER7962 Rev. C

ER7961 Rev. C

MEDICATION GUIDE

XARELTO ®(zah-REL-toe)
(rivaroxaban)
tablets

XARELTO ®(zah-REL-toe)
(rivaroxaban)
oral suspension

What is the most important information I should know about XARELTO?
XARELTO may cause serious side effects, including:

- Increased risk of blood clots if you stop taking XARELTO.People with atrial fibrillation (a type of irregular heart beat) that is not caused by a heart valve problem (non-valvular) are at an increased risk of forming a blood clot in the heart, which can travel to the brain, causing a stroke, or to other parts of the body. XARELTO lowers your chance of having a stroke by helping to prevent clots from forming. If you stop taking XARELTO, you may have increased risk of forming a clot in your blood.
  Do not stop taking XARELTO without talking to the doctor who prescribes it for you. Stopping XARELTO increases your risk of having a stroke.If you have to stop taking XARELTO, your doctor may prescribe another blood thinner medicine to prevent a blood clot from forming.
- Increased risk of bleeding.XARELTO can cause bleeding which can be serious and may lead to death. This is because XARELTO is a blood thinner medicine (anticoagulant) that lowers blood clotting. During treatment with XARELTO you are likely to bruise more easily, and it may take longer for bleeding to stop. You may have a higher risk of bleeding if you take XARELTO and have certain other medical problems.
  You may have a higher risk of bleeding if you take XARELTO and take other medicines that increase your risk of bleeding, including:Tell your doctorif you take any of these medicines. Ask your doctor or pharmacist if you are not sure if your medicine is one listed above.
  Call your doctor or get medical help right away if you or your child develop any of these signs or symptoms of bleeding:
  - aspirin or aspirin containing products
  - long-term (chronic) use of non-steroidal anti-inflammatory drugs (NSAIDs)
  - warfarin sodium (Coumadin®, Jantoven®)
  - any medicine that contains heparin
  - clopidogrel (Plavix ®)
  - selective serotonin reuptake inhibitors (SSRIs) or serotonin norepinephrine reuptake inhibitors (SNRIs)
  - other medicines to prevent or treat blood clots
  - unexpected bleeding or bleeding that lasts a long time, such as:
    - nose bleeds that happen often
    - unusual bleeding from the gums
    - menstrual bleeding that is heavier than normal or vaginal bleeding
  - bleeding that is severe or you cannot control
  - red, pink or brown urine
  - bright red or black stools (looks like tar)
  - cough up blood or blood clots
  - vomit blood or your vomit looks like "coffee grounds"
  - headaches, feeling dizzy or weak
  - pain, swelling, or new drainage at wound sites
  - left upper belly (abdominal) pain, pain below the left rib cage or at the tip of your left shoulder or diffuse abdominal discomfort (these may be symptoms of rupture of the spleen)
- Spinal or epidural blood clots (hematoma).People who take a blood thinner medicine (anticoagulant) like XARELTO, and have medicine injected into their spinal and epidural area, or have a spinal puncture have a risk of forming a blood clot that can cause long-term or permanent loss of the ability to move (paralysis). Your risk of developing a spinal or epidural blood clot is higher if: If you take XARELTO and receive spinal anesthesia or have a spinal puncture, your doctor should watch you closely for symptoms of spinal or epidural blood clots.
  Tell your doctor right away if you have:
  - a thin tube called an epidural catheter is placed in your back to give you certain medicine
  - you take NSAIDs or a medicine to prevent blood from clotting
  - you have a history of difficult or repeated epidural or spinal punctures
  - you have a history of problems with your spine or have had surgery on your spine

- back pain
- tingling
- numbness

- muscle weakness (especially in your legs and feet)
- loss of control of the bowels or bladder (incontinence)

XARELTO is not for use in people with artificial heart valves.
XARELTO is not for use in people with antiphospholipid syndrome (APS), especially with positive triple antibody testing.

What is XARELTO?
XARELTO is a prescription medicine used to:

- reduce the risk of stroke and blood clots in adults who have a medical condition called atrial fibrillation that is not caused by a heart valve problem. With atrial fibrillation, part of the heart does not beat the way it should. This can lead to the formation of blood clots, which can travel to the brain, causing a stroke, or to other parts of the body.
- treat blood clots in the veins of your legs (deep vein thrombosis or DVT) or lungs (pulmonary embolism or PE)
- reduce the risk of blood clots from happening again in adults who continue to be at risk for DVT or PE after receiving treatment for blood clots for at least 6 months.
- help prevent a blood clot in the legs and lungs of adults who have just had hip or knee replacement surgery.
- help prevent blood clots in certain adults hospitalized for an acute illness and after discharge who are at risk of getting blood clots because of the loss of or decreased ability to move around (mobility) and other risks for getting blood clots and who do not have a high risk of bleeding.

XARELTO is used with low dose aspirin to:

- reduce the risk of serious heart problems, heart attack and stroke in adults with coronary artery disease (a condition where the blood supply to the heart is reduced or blocked).
- reduce the risk of a sudden decrease in blood flow to the legs, major amputation, serious heart problems or stroke in adults with peripheral artery disease (a condition where the blood flow to the legs is reduced) and includes adults who have recently had a procedure to improve blood flow to the legs.

XARELTO is used in children to:

- treat blood clots or reduce the risk of blood clots from happening again in children from birth to less than 18 years, after receiving at least 5 days of treatment with injectable or intravenous medicines used to treat blood clots.
- help prevent blood clots in children 2 years and older with congenital heart disease after the Fontan procedure.

XARELTO was not studied and is not recommended in children less than 6 months of age who:

- were less than 37 weeks of growth (gestation) at birth
- had less than 10 days of oral feeding, or
- had a body weight of less than 5.7 pounds (2.6 kg)

Do not take XARELTO if you or your child:

- currently have certain types of abnormal bleeding. Talk to your doctor before taking XARELTO if you currently have unusual bleeding.
- are allergic to rivaroxaban or any of the ingredients in XARELTO. See the end of this Medication Guide for a complete list of ingredients in XARELTO.

Before taking XARELTO, tell your doctor about all of your medical conditions, including if you or your child:

- have or ever had bleeding problems
- have liver or kidney problems
- have antiphospholipid syndrome (APS)
- are pregnant or plan to become pregnant. It is not known if XARELTO will harm your unborn baby.
  - Tell your doctorright away if you become pregnant during treatment with XARELTO. Taking XARELTO while you are pregnant may increase the risk of bleeding in you or in your unborn baby.
  - Females who are able to become pregnant: Talk with your doctor about pregnancy planning during treatment with XARELTO. Talk with your doctor about your risk for severe uterine bleeding if you are treated with blood thinner medicines, including XARELTO.
  - If you take XARELTO during pregnancy tell your doctorright away if you have any signs or symptoms of bleeding or blood loss. See "What is the most important information I should know about XARELTO?" for signs and symptoms of bleeding.
- are breastfeeding or plan to breastfeed. XARELTO can pass into your breast milk. Talk to your doctor about the best way to feed your baby during treatment with XARELTO.

Tell all of your doctors and dentiststhat you or your child are taking XARELTO. They should talk to the doctor who prescribed XARELTO for you before you have any surgery, medical or dental procedure.
Tell your doctor about all the medicines you or your child take,including prescription and over-the-counter medicines, vitamins, and herbal supplements.
Some of your other medicines may affect the way XARELTO works, causing side effects. Certain medicines may increase your risk of bleeding. See "What is the most important information I should know about XARELTO?"
Especially tell your doctor if you or your child take:

- ketoconazole
- erythromycin
- phenytoin
- St. John's wort

- ritonavir
- carbamazepine
- rifampin

How should I take XARELTO?

- Take XARELTO exactly as prescribed by your doctor.
- Do not change your dose or stop taking XARELTO unless your doctor tells you to.Your doctor may change your dose if needed.
- Your doctor will decide how long you should take XARELTO.
- XARELTO may need to be stopped for one or more days before any surgery or medical or dental procedure. Your doctor will tell you when to stop taking XARELTO and when to start taking XARELTO again after your surgery or procedure.
- If you need to stop taking XARELTO for any reason, talk to the doctor who prescribed XARELTO to you to find out when you should stop taking it. Do not stop taking XARELTO without first talking to the doctor who prescribes it to you.
- If you have difficulty swallowing XARELTO tablets whole, talk to your doctor about other ways to take XARELTO.
- Do not run out of XARELTO. Refill your prescription of XARELTO before you run out. When leaving the hospital following a hip or knee replacement, be sure that you will have XARELTO available to avoid missing any doses.
- If you take too much XARELTO, go to the nearest hospital emergency room or call your doctor right away.

If you take XARELTO for:

- Atrial fibrillation that is not caused by a heart valve problem:
  - Take XARELTO 1 time a day with your evening meal.
  - If you miss a dose of XARELTO, take it as soon as you remember on the same day. Take your next dose at your regularly scheduled time.
- Blood clots in the veins of your legs or lungs:
  - Take XARELTO 1 or 2 times a dayas prescribed by your doctor.
  - For the 10 mg dose, take XARELTO with or without food.
  - For the 15 mg and 20 mg doses, take XARELTO with food at the same time each day.
  - If you miss a dose:
    - If you take the 15 mg dose of XARELTO 2 times a day (a total of 30 mg of XARELTO in 1 day): Take XARELTO as soon as you remember on the same day. You may take 2 doses at the same time to make up for the missed dose. Take your next dose at your regularly scheduled time.
    - If you take XARELTO 1 time a day:Take XARELTO as soon as you remember on the same day. Take your next dose at your regularly scheduled time.
- Hip or knee replacement surgery:
  - Take XARELTO 1 time a day with or without food.
  - If you miss a dose of XARELTO, take it as soon as you remember on the same day. Take your next dose at your regularly scheduled time.
- Blood clots in people hospitalized for an acute illness:
  - Take XARELTO 1 time a day, with or without food, while you are in the hospital and after you are discharged as prescribed by your doctor.
  - If you miss a dose of XARELTO, take it as soon as you remember on the same day. Take your next dose at your regularly scheduled time.
- Reducing the risk of serious heart problems, heart attack and stroke in coronary artery disease:
  - Take XARELTO 2.5 mg 2 times a day with or without food.
  - If you miss a dose of XARELTO, take your next dose at your regularly scheduled time.
  - Take aspirin 75 to 100 mg once daily as instructed by your doctor.
- Reducing the risk of a sudden decrease in blood flow to the legs, major amputation, serious heart problems or stroke in people with peripheral artery disease including those who have recently had a procedure to improve blood flow to the legs:
  - Take XARELTO 2.5 mg 2 times a day with or without food.
  - If you miss a dose of XARELTO, take your next dose at your regularly scheduled time.
  - Take aspirin 75 mg to 100 mg 1 time a day as instructed by your doctor.

For children who take XARELTO:

- The dose of XARELTO depends on your child's body weight and will be calculated by your child's doctor. Your child's doctor will tell you if XARELTO can be given to your child with or without food.
- The adult caregiver should give the dose.
- If your child is taking the tablet, the tablet should be taken whole and should not be split in an attempt to provide a lower dose of XARELTO.
- If your child is taking the oral suspension, use the syringes provided in the original carton. The suspension will be prepared by the pharmacy. See the Instructions for Use included in the carton on how to properly give a dose of XARELTO oral suspension to your child.
- Do not switch between the XARELTO oral suspension or tablet without first talking to your doctor.
- If your child vomits or spits up:
  - right after or within 30 minutes of taking the oral suspension, give a new full dose.
  - more than 30 minutes after taking the oral suspension, do not give the dose again. Give the next dose at the regularly scheduled time.
  - if vomiting or spitting up persists, contact your child's doctor right away.
- If your child misses a dose:
  - If your child is taking XARELTO 1 time a day, give the dose as soon as you remember on the same day. If this is not possible, skip this dose and give the next dose at the regularly scheduled time.
  - If your child is taking XARELTO 2 times a day, give the missed morning dose as soon as you remember. You may give the missed morning dose together with the evening dose. However, a missed evening dose can only be taken in the same evening.
  - If your child is taking XARELTO 3 times a day, skip the missed dose and give the next dose at the regularly scheduled time.

What are the possible side effects of XARELTO?
XARELTO may cause serious side effects:

- See "What is the most important information I should know about XARELTO?"

The most common side effect of XARELTO in adults was bleeding.
The most common side effects of XARELTO in children include:

- bleeding
- vomiting

- cough
- inflamed stomach and gut

Call your doctor for medical advice about side effects. You may report side effects to FDA at 1 800-FDA-1088.

How should I store XARELTO?

- Store XARELTO tablets and suspension at room temperature between 68 °F to 77 °F (20 °C to 25 °C).
- Store syringes and bottle upright in the original carton for XARELTO suspension.
- Do notfreeze XARELTO suspension.

Keep XARELTO and all medicines out of the reach of children.
Discard XARELTO suspension after "Discard after" date written on the bottle.

General information about the safe and effective use of XARELTO.
Medicines are sometimes prescribed for purposes other than those listed in a Medication Guide. Do not use XARELTO for a condition for which it was not prescribed. Do not give XARELTO to other people, even if they have the same symptoms that you have. It may harm them. You can ask your pharmacist or doctor for information about XARELTO that is written for health professionals.

What are the ingredients in XARELTO?
Active ingredient:rivaroxaban
Inactive ingredients tablets:
croscarmellose sodium, hypromellose, lactose monohydrate, magnesium stearate, microcrystalline cellulose, and sodium lauryl sulfate.
The proprietary film coating mixture for XARELTO 2.5 mg tablets is Opadry®Light Yellow and contains: ferric oxide yellow, hypromellose, polyethylene glycol 3350, and titanium dioxide.
The proprietary film coating mixture for XARELTO 10 mg tablets is Opadry®Pink and contains: ferric oxide red, hypromellose, polyethylene glycol 3350, and titanium dioxide.
The proprietary film coating mixture for XARELTO 15 mg tablets is Opadry®Red and contains: ferric oxide red, hypromellose, polyethylene glycol 3350, and titanium dioxide.
The proprietary film coating mixture for XARELTO 20 mg tablets is Opadry®II Dark Red and contains: ferric oxide red, polyethylene glycol 3350, polyvinyl alcohol (partially hydrolyzed), talc, and titanium dioxide.
Inactive ingredients for oral suspension:
anhydrous citric acid, hypromellose, mannitol, microcrystalline cellulose and carboxymethylcellulose sodium, sodium benzoate, sucralose, sweet and creamy flavor, and xanthan gum.
Manufactured for: Janssen Pharmaceuticals, Inc., Titusville, NJ 08560, USA. Licensed from: Bayer HealthCare AG 51368 Leverkusen, Germany
For patent information: www.janssenpatents.com
© Johnson & Johnson and its affiliates 2011-2021, 2025
Xarelto is a registered trademark of Bayer Aktiengesellschaft.
For more information go to www.XARELTO-US.com or call 1-800-526-7736.

Distributed By:

Cardinal Health

Dublin, OH 43017

L49750740324

ER7962 Rev. C

ER7961 Rev. C

This Medication Guide has been approved by the U.S. Food and Drug Administration

Revised: 06/2025

Package/Label Display Panel

NDC 55154-1422-0

XARELTO® Tablets 10 mg

(Rivaroxaban)

10 TABLETS

Package/Label Display Panel

Contains Approximately

2070 Tablets

XARELTO®

(rivaroxaban) tablets

15 mg

Each tablet contains:

15 mg of rivaroxaban.

Dispense the Medication Guide to each

patient.

Rx Only

WARNING: Keep out of reach of

children.

Package/Label Display Panel

Contains Approximately

4440 Tablets

XARELTO®

(rivaroxaban) tablets

20 mg

Each tablet contains:

20 mg of rivaroxaban.

Dispense the Medication Guide to each

patient.

Rx Only

WARNING: Keep out of reach of

children.